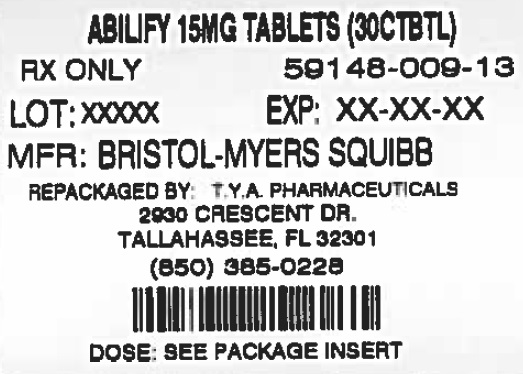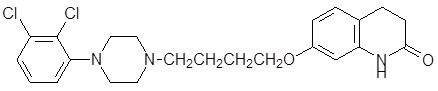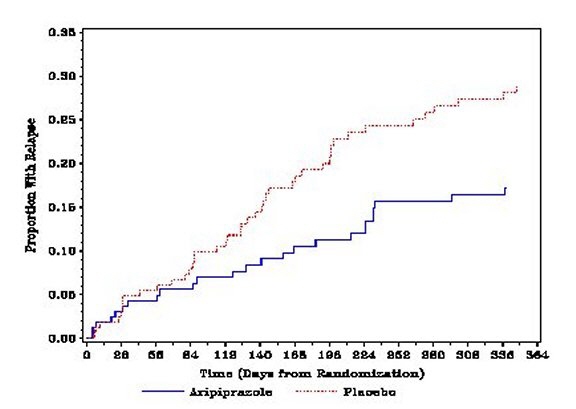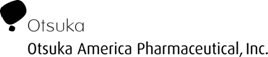 DRUG LABEL: ABILIFY
NDC: 64725-0009 | Form: TABLET
Manufacturer: TYA Pharmaceuticals
Category: prescription | Type: HUMAN PRESCRIPTION DRUG LABEL
Date: 20140703

ACTIVE INGREDIENTS: ARIPIPRAZOLE 15 mg/1 1
INACTIVE INGREDIENTS: STARCH, CORN; HYDROXYPROPYL CELLULOSE (TYPE H); LACTOSE MONOHYDRATE; MAGNESIUM STEARATE; CELLULOSE, MICROCRYSTALLINE; FERRIC OXIDE RED; FERRIC OXIDE YELLOW; FD&C BLUE NO. 2; ALUMINUM OXIDE

HIGHLIGHTS OF PRESCRIBING INFORMATION

These highlights do not include all the information needed to use ABILIFY safely and effectively. See full prescribing information for ABILIFY. ABILIFY (aripiprazole) Tablets ABILIFY DISCMELT (aripiprazole) Orally Disintegrating Tablets ABILIFY (aripiprazole) Oral Solution ABILIFY (aripiprazole) Injection FOR INTRAMUSCULAR USE ONLY Initial U.S. Approval: 2002
®
®
®
®

RECENT MAJOR CHANGES

Dosage and Administration, Pediatric (6 to 17 years), Irritability Associated with Autistic Disorder - 06/2014 (2.4)

WARNING: INCREASED MORTALITY IN ELDERLY PATIENTS WITH DEMENTIA-RELATED PSYCHOSIS and SUICIDALTHOUGHTS AND BEHAVIORS

WARNING: INCREASED MORTALITY IN ELDERLY PATIENTS WITH DEMENTIA-RELATED PSYCHOSIS and SUICIDAL THOUGHTS AND BEHAVIORS

See full prescribing information for complete boxed warning.

1 INDICATIONS AND USAGE

ABILIFY is an atypical antipsychotic indicated as oral formulations for the:

Treatment of schizophrenia (1.1)

- Adults: Efficacy was established in four 4-6 week trials and one maintenance trial in patients with schizophrenia (14.1)
- Adolescents (ages 13-17): Efficacy was established in one 6-week trial in patients with schizophrenia (14.1)

Acute treatment of manic or mixed episodes associated with bipolar I disorder as monotherapy and as an adjunct to lithium or valproate (1.2)

- Adults: Efficacy was established in four 3-week monotherapy trials and one 6-week adjunctive trial in patients with manic or mixed episodes (14.2)
- Pediatric Patients (ages 10-17): Efficacy was established in one 4-week monotherapy trial in patients with manic or mixed episodes (14.2)

Maintenance treatment of bipolar I disorder, both as monotherapy and as an adjunct to lithium or valproate (1.2)

- Adults: Efficacy was established in one maintenance monotherapy trial and in one maintenance adjunctive trial (14.2)

Adjunctive treatment of major depressive disorder (MDD) (1.3)

- Adults: Efficacy was established in two 6-week trials in patients with MDD who had an inadequate response to antidepressant therapy during the current episode (14.3)

Treatment of irritability associated with autistic disorder (1.4)

- Pediatric Patients (ages 6-17 years): Efficacy was established in two 8-week trials in patients with autistic disorder (14.4)

as an injection for the:

Acute treatment of agitation associated with schizophrenia or bipolar I disorder (1.5)

- Adults: Efficacy was established in three 24-hour trials in agitated patients with schizophrenia or manic/mixed episodes of bipolar I disorder (14.5)

2 DOSAGE AND ADMINISTRATION

 | Initial Dose | Recommended Dose | Maximum Dose
Schizophrenia – adults (2.1) | 10-15 mg /day | 10-15 mg /day | 30 mg /day
Schizophrenia – adolescents (2.1) | 2 mg /day | 10 mg /day | 30 mg /day
Bipolar mania – adults: monotherapy (2.2) | 15 mg /day | 15 mg /day | 30 mg /day
Bipolar mania – adults: adjunct to lithium or valproate (2.2) | 10-15 mg /day | 15 mg /day | 30 mg /day
Bipolar mania – pediatric patients: monotherapy or as an adjunct to lithium or valproate (2.2) | 2 mg /day | 10 mg /day | 30 mg /day
As an adjunct to antidepressants for the treatment of major depressive disorder – adults (2.3) | 2-5 mg /day | 5-10 mg /day | 15 mg /day
Irritability associated with autistic disorder – pediatric patients (2.4) | 2 mg /day | 5-10 mg /day | 15 mg /day
Agitation associated with schizophrenia or bipolar mania – adults (2.5) | 9.75 mg /1.3 mL injected IM |  | 30 mg /day injected IM

- Oral formulations: Administer once daily without regard to meals (2)
- IM injection: Wait at least 2 hours between doses. Maximum daily dose 30 mg (2.5)

3 DOSAGE FORMS AND STRENGTHS

- Tablets: 2 mg, 5 mg, 10 mg, 15 mg, 20 mg, and 30 mg (3)
- Orally Disintegrating Tablets: 10 mg and 15 mg (3)
- Oral Solution: 1 mg/mL (3)
- Injection: 9.75 mg/1.3 mL single-dose vial (3)

4 CONTRAINDICATIONS

Known hypersensitivity to ABILIFY (4)

5 WARNINGS AND PRECAUTIONS

- Increased incidence of cerebrovascular adverse events (eg, stroke, transient ischemic attack, including fatalities) Elderly Patients with Dementia-Related Psychosis:(5.1)
- Increased risk of suicidality in children, adolescents, and young adults with major depressive disorder Suicidality and Antidepressants:(5.2)
- Manage with immediate discontinuation and close monitoring Neuroleptic Malignant Syndrome:(5.3)
- Discontinue if clinically appropriate Tardive Dyskinesia:(5.4)
- Atypical antipsychotic drugs have been associated with metabolic changes that include hyperglycemia/diabetes mellitus, dyslipidemia, and body weight gain Metabolic Changes:(5.5)
  - Monitor glucose regularly in patients with and at risk for diabetes Hyperglycemia/Diabetes Mellitus:(5.5)
  - Undesirable alterations in lipid levels have been observed in patients treated with atypical antipsychotics Dyslipidemia:(5.5)
  - Weight gain has been observed with atypical antipsychotic use. Monitor weight Weight Gain:(5.5)
- Use with caution in patients with known cardiovascular or cerebrovascular disease Orthostatic Hypotension:(5.6)
- have been reported with antipsychotics including ABILIFY. Patients with a history of a clinically significant low white blood cell count (WBC) or a drug-induced leukopenia/neutropenia should have their complete blood count (CBC) monitored frequently during the first few months of therapy and discontinuation of ABILIFY should be considered at the first sign of a clinically significant decline in WBC in the absence of other causative factors Leukopenia, Neutropenia, and Agranulocytosis:(5.7)
- Use cautiously in patients with a history of seizures or with conditions that lower the seizure threshold Seizures/Convulsions:(5.8)
- Use caution when operating machinery Potential for Cognitive and Motor Impairment:(5.9)
- The possibility of a suicide attempt is inherent in schizophrenia and bipolar disorder. Closely supervise high-risk patients Suicide:(5.11)

6 ADVERSE REACTIONS

Commonly observed adverse reactions (incidence ≥5% and at least twice that for placebo) were : (6.2)

- Adult patients with schizophrenia: akathisia
- Pediatric patients (13 to 17 years) with schizophrenia: extrapyramidal disorder, somnolence, and tremor
- Adult patients (monotherapy) with bipolar mania: akathisia, sedation, restlessness, tremor, and extrapyramidal disorder
- Adult patients (adjunctive therapy with lithium or valproate) with bipolar mania: akathisia, insomnia, and extrapyramidal disorder
- Pediatric patients (10 to 17 years) with bipolar mania: somnolence, extrapyramidal disorder, fatigue, nausea, akathisia, blurred vision, salivary hypersecretion, and dizziness
- Adult patients with major depressive disorder (adjunctive treatment to antidepressant therapy): akathisia, restlessness, insomnia, constipation, fatigue, and blurred vision
- Pediatric patients (6 to 17 years) with autistic disorder: sedation, fatigue, vomiting, somnolence, tremor, pyrexia, drooling, decreased appetite, salivary hypersecretion, extrapyramidal disorder, and lethargy
- Adult patients with agitation associated with schizophrenia or bipolar mania: nausea

To report SUSPECTED ADVERSE REACTIONS, contact Bristol-Myers Squibb at 1-800-721-5072 or FDA at 1-800-FDA-1088 or www.fda.gov/medwatch

7 DRUG INTERACTIONS

- ABILIFY drug concentrations; reduce ABILIFY dose to one-half of the usual dose when used concomitantly , , except when used as adjunctive treatment with antidepressants . If a strong CYP3A4 inhibitor and strong CYP2D6 inhibitor are coadministered or a known CYP2D6 poor metabolizer is receiving a concomitant strong CYP3A4 inhibitor, the ABILIFY dose should be reduced to one-quarter (25%) of the usual dose , . Strong CYP3A4 (eg, ketoconazole) or CYP2D6 (eg, fluoxetine) inhibitors will increase (2.67.1) (2.6) (2.612.3)
- ABILIFY drug concentrations; double ABILIFY dose when used concomitantly , CYP3A4 inducers (eg, carbamazepine) will decrease (2.67.1)

FULL PRESCRIBING INFORMATION

WARNING: INCREASED MORTALITY IN ELDERLY PATIENTS WITH DEMENTIA-RELATED PSYCHOSIS and SUICIDALTHOUGHTS AND BEHAVIORS

Elderly patients with dementia-related psychosis treated with antipsychotic drugs are at an increased risk of death. Analyses of seventeen placebo-controlled trials (modal duration of 10 weeks), largely in patients taking atypical antipsychotic drugs, revealed a risk of death in drug-treated patients of between 1.6 to 1.7 times the risk of death in placebo-treated patients. Over the course of a typical 10-week controlled trial, the rate of death in drug-treated patients was about 4.5%, compared to a rate of about 2.6% in the placebo group. Although the causes of death were varied, most of the deaths appeared to be either cardiovascular (eg, heart failure, sudden death) or infectious (eg, pneumonia) in nature. Observational studies suggest that, similar to atypical antipsychotic drugs, treatment with conventional antipsychotic drugs may increase mortality. The extent to which the findings of increased mortality in observational studies may be attributed to the antipsychotic drug as opposed to some characteristic(s) of the patients is not clear. ABILIFY (aripiprazole) is not approved for the treatment of patients with dementia-related psychosis . [see WARNINGS AND PRECAUTIONS ] (5.1)

Antidepressants increased the risk compared to placebo of suicidal thinking and behavior (suicidality) in children, adolescents, and young adults in short-term studies of major depressive disorder (MDD) and other psychiatric disorders. Anyone considering the use of adjunctive ABILIFY or any other antidepressant in a child, adolescent, or young adult must balance this risk with the clinical need. Short-term studies did not show an increase in the risk of suicidality with antidepressants compared to placebo in adults beyond age 24; there was a reduction in risk with antidepressants compared to placebo in adults aged 65 and older. Depression and certain other psychiatric disorders are themselves associated with increases in the risk of suicide. Patients of all ages who are started on antidepressant therapy should be monitored appropriately and observed closely for clinical worsening, suicidality, or unusual changes in behavior. Families and caregivers should be advised of the need for close observation and communication with the prescriber. ABILIFY is not approved for use in pediatric patients with depression . [see WARNINGS AND PRECAUTIONS ] (5.2)

1 INDICATIONS AND USAGE

1.1 Schizophrenia

ABILIFY is indicated for the treatment of schizophrenia. The efficacy of ABILIFY was established in four 4-6 week trials in adults and one 6-week trial in adolescents (13 to 17 years). Maintenance efficacy was demonstrated in one trial in adults and can be extrapolated to adolescents . [see CLINICAL STUDIES ] (14.1)

1.2 Bipolar I Disorder

Acute Treatment of Manic and Mixed Episodes

ABILIFY is indicated for the acute treatment of manic and mixed episodes associated with bipolar I disorder, both as monotherapy and as an adjunct to lithium or valproate. Efficacy as monotherapy was established in four 3-week monotherapy trials in adults and one 4-week monotherapy trial in pediatric patients (10 to 17 years). Efficacy as adjunctive therapy was established in one 6-week adjunctive trial in adults . [see CLINICAL STUDIES ] (14.2)

Maintenance Treatment of Bipolar I Disorder

ABILIFY is indicated for the maintenance treatment of bipolar I disorder, both as monotherapy and as an adjunct to either lithium or valproate. Maintenance efficacy was demonstrated in one monotherapy maintenance trial and in one adjunctive maintenance trial in adults . [see CLINICAL STUDIES ] (14.2)

1.3 Adjunctive Treatment of Major Depressive Disorder

ABILIFY is indicated for use as an adjunctive therapy to antidepressants for the treatment of major depressive disorder (MDD). Efficacy was established in two 6-week trials in adults with MDD who had an inadequate response to antidepressant therapy during the current episode . [see CLINICAL STUDIES ] (14.3)

1.4 Irritability Associated with Autistic Disorder

ABILIFY is indicated for the treatment of irritability associated with autistic disorder. Efficacy was established in two 8-week trials in pediatric patients (aged 6 to 17 years) with irritability associated with autistic disorder (including symptoms of aggression towards others, deliberate self-injuriousness, temper tantrums, and quickly changing moods) . [see CLINICAL STUDIES ] (14.4)

1.5 Agitation Associated with Schizophrenia or Bipolar Mania

ABILIFY Injection is indicated for the acute treatment of agitation associated with schizophrenia or bipolar disorder, manic or mixed. “Psychomotor agitation” is defined in DSM-IV as “excessive motor activity associated with a feeling of inner tension.” Patients experiencing agitation often manifest behaviors that interfere with their diagnosis and care (eg, threatening behaviors, escalating or urgently distressing behavior, or self-exhausting behavior), leading clinicians to the use of intramuscular antipsychotic medications to achieve immediate control of the agitation. Efficacy was established in three short-term (24-hour) trials in adults . [see CLINICAL STUDIES ] (14.5)

1.6 Special Considerations in Treating Pediatric Schizophrenia, Bipolar I Disorder, and Irritability Associated with Autistic Disorder

Psychiatric disorders in children and adolescents are often serious mental disorders with variable symptom profiles that are not always congruent with adult diagnostic criteria. It is recommended that psychotropic medication therapy for pediatric patients only be initiated after a thorough diagnostic evaluation has been conducted and careful consideration given to the risks associated with medication treatment. Medication treatment for pediatric patients with schizophrenia, bipolar I disorder, and irritability associated with autistic disorder is indicated as part of a total treatment program that often includes psychological, educational, and social interventions.

2 DOSAGE AND ADMINISTRATION

2.1 Schizophrenia

DOSAGE AND ADMINISTRATION

Adults

Dose Selection: The recommended starting and target dose for ABILIFY is 10 mg/day or 15 mg/day administered on a once-a-day schedule without regard to meals. ABILIFY has been systematically evaluated and shown to be effective in a dose range of 10 mg/day to 30 mg/day, when administered as the tablet formulation; however, doses higher than 10 mg/day or 15 mg/day were not more effective than 10 mg/day or 15 mg/day. Dosage increases should generally not be made before 2 weeks, the time needed to achieve steady-state . [see CLINICAL STUDIES ] (14.1)

Maintenance Treatment: Maintenance of efficacy in schizophrenia was demonstrated in a trial involving patients with schizophrenia who had been symptomatically stable on other antipsychotic medications for periods of 3 months or longer. These patients were discontinued from those medications and randomized to either ABILIFY 15 mg/day or placebo, and observed for relapse . Patients should be periodically reassessed to determine the continued need for maintenance treatment. [see CLINICAL STUDIES ] (14.1)

DOSAGE AND ADMINISTRATION

Adolescents

Dose Selection: The recommended target dose of ABILIFY is 10 mg/day. Aripiprazole was studied in adolescent patients 13 to 17 years of age with schizophrenia at daily doses of 10 mg and 30 mg. The starting daily dose of the tablet formulation in these patients was 2 mg, which was titrated to 5 mg after 2 days and to the target dose of 10 mg after 2 additional days. Subsequent dose increases should be administered in 5 mg increments. The 30 mg/day dose was not shown to be more efficacious than the 10 mg/day dose. ABILIFY can be administered without regard to meals . [see CLINICAL STUDIES ] (14.1)

Maintenance Treatment: The efficacy of ABILIFY for the maintenance treatment of schizophrenia in the adolescent population has not been evaluated. While there is no body of evidence available to answer the question of how long the adolescent patient treated with ABILIFY should be maintained on the drug, maintenance efficacy can be extrapolated from adult data along with comparisons of aripiprazole pharmacokinetic parameters in adult and pediatric patients. Thus, it is generally recommended that responding patients be continued beyond the acute response, but at the lowest dose needed to maintain remission. Patients should be periodically reassessed to determine the need for maintenance treatment.

DOSAGE AND ADMINISTRATION

Switching from Other Antipsychotics

There are no systematically collected data to specifically address switching patients with schizophrenia from other antipsychotics to ABILIFY or concerning concomitant administration with other antipsychotics. While immediate discontinuation of the previous antipsychotic treatment may be acceptable for some patients with schizophrenia, more gradual discontinuation may be most appropriate for others. In all cases, the period of overlapping antipsychotic administration should be minimized.

2.2 Bipolar I Disorder

Acute Treatment of Manic and Mixed Episodes

Adults: The recommended starting dose in adults is 15 mg given once daily as monotherapy and 10 mg to 15 mg given once daily as adjunctive therapy with lithium or valproate. ABILIFY can be given without regard to meals. The recommended target dose of ABILIFY is 15 mg/day, as monotherapy or as adjunctive therapy with lithium or valproate. The dose may be increased to 30 mg/day based on clinical response. The safety of doses above 30 mg/day has not been evaluated in clinical trials.

Pediatrics: The recommended starting dose in pediatric patients (10 to 17 years) as monotherapy is 2 mg/day, with titration to 5 mg/day after 2 days, and a target dose of 10 mg/day after 2 additional days. Recommended dosing as adjunctive therapy to lithium or valproate is the same. Subsequent dose increases, if needed, should be administered in 5 mg/day increments. ABILIFY can be given without regard to meals . [see CLINICAL STUDIES ] (14.2)

Maintenance Treatment

The recommended dose for maintenance treatment, whether as monotherapy or as adjunctive therapy, is the same dose needed to stabilize patients during acute treatment, both for adult and pediatric patients. Patients should be periodically reassessed to determine the continued need for maintenance treatment [see CLINICAL STUDIES ]. (14.2)

2.3 Adjunctive Treatment of Major Depressive Disorder

DOSAGE AND ADMINISTRATION

Adults

Dose Selection: The recommended starting dose for ABILIFY as adjunctive treatment for patients already taking an antidepressant is 2 mg/day to 5 mg/day. The efficacy of ABILIFY as an adjunctive therapy for major depressive disorder was established within a dose range of 2 mg/day to 15 mg/day. Dose adjustments of up to 5 mg/day should occur gradually, at intervals of no less than 1 week . [see CLINICAL STUDIES ] (14.3)

Maintenance Treatment: The efficacy of ABILIFY for the adjunctive maintenance treatment of major depressive disorder has not been evaluated. While there is no body of evidence available to answer the question of how long the patient treated with ABILIFY should be maintained, patients should be periodically reassessed to determine the continued need for maintenance treatment.

2.4 Irritability Associated with Autistic Disorder

Pediatric Patients

Dose Selection: The efficacy of aripiprazole has been established in the treatment of pediatric patients 6 to 17 years of age with irritability associated with autistic disorder at doses of 5 mg/day to 15 mg/day. The dosage of ABILIFY should be individualized according to tolerability and response.

Dosing should be initiated at 2 mg/day. The dose should be increased to 5 mg/day, with subsequent increases to 10 mg/day or 15 mg/day if needed. Dose adjustments of up to 5 mg/day should occur gradually, at intervals of no less than 1 week . [see CLINICAL STUDIES ] (14.4)

. Maintenance Treatment: In a clinical trial with ABILIFY conducted in children and adolescents (6 to 17 years of age), the efficacy of ABILIFY for the maintenance treatment of irritability associated with autistic disorder was not established [see Use in Specific Populations ]. Patients should be periodically reassessed to determine the continued need for maintenance treatment (8.4)

2.5 Agitation Associated with Schizophrenia or Bipolar Mania (Intramuscular Injection)

DOSAGE AND ADMINISTRATION

Adults

Dose Selection: The recommended dose in these patients is 9.75 mg. The effectiveness of aripiprazole injection in controlling agitation in schizophrenia and bipolar mania was demonstrated over a dose range of 5.25 mg to 15 mg. No additional benefit was demonstrated for 15 mg compared to 9.75 mg. A lower dose of 5.25 mg may be considered when clinical factors warrant. If agitation warranting a second dose persists following the initial dose, cumulative doses up to a total of 30 mg/day may be given. However, the efficacy of repeated doses of aripiprazole injection in agitated patients has not been systematically evaluated in controlled clinical trials. The safety of total daily doses greater than 30 mg or injections given more frequently than every 2 hours have not been adequately evaluated in clinical trials . [see CLINICAL STUDIES ] (14.5)

If ongoing aripiprazole therapy is clinically indicated, oral aripiprazole in a range of 10 mg/day to 30 mg/day should replace aripiprazole injection as soon as possible . [see DOSAGE AND ADMINISTRATION and ] (2.12.2)

Administration of ABILIFY Injection

To administer ABILIFY Injection, draw up the required volume of solution into the syringe as shown in Table 1. Discard any unused portion.

Table 1: ABILIFY Injection Dosing Recommendations
Single-Dose | Required Volume of Solution
5.25 mg | 0.7 mL
9.75 mg | 1.3 mL
15 mg | 2 mL

ABILIFY Injection is intended for intramuscular use only. Do not administer intravenously or subcutaneously. Inject slowly, deep into the muscle mass.

Parenteral drug products should be inspected visually for particulate matter and discoloration prior to administration, whenever solution and container permit.

2.6 Dosage Adjustment

Dosage adjustments in adults are not routinely indicated on the basis of age, gender, race, or renal or hepatic impairment status . [see USE IN SPECIFIC POPULATIONS - ] (8.48.10)

When concomitant administration of aripiprazole with strong CYP3A4 inhibitors such as ketoconazole or clarithromycin is indicated, the aripiprazole dose should be reduced to one-half of the usual dose. When the CYP3A4 inhibitor is withdrawn from the combination therapy, the aripiprazole dose should then be increased . Dosage adjustment for patients taking aripiprazole concomitantly with strong CYP3A4 inhibitors:[see DRUG INTERACTIONS ] (7.1)
When concomitant administration of potential CYP2D6 inhibitors such as quinidine, fluoxetine, or paroxetine with aripiprazole occurs, aripiprazole dose should be reduced at least to one-half of its normal dose. When the CYP2D6 inhibitor is withdrawn from the combination therapy, the aripiprazole dose should then be increased . When adjunctive ABILIFY is administered to patients with major depressive disorder, ABILIFY should be administered without dosage adjustment as specified in . Dosage adjustment for patients taking aripiprazole concomitantly with potential CYP2D6 inhibitors:[see DRUG INTERACTIONS ] (7.1) DOSAGE AND ADMINISTRATION (2.3)
When concomitant administration of aripiprazole with strong inhibitors of CYP3A4 (such as ketoconazole or clarithromycin) and CYP2D6 (such as quinidine, fluoxetine, or paroxetine) is indicated, the aripiprazole dose should be reduced to one-quarter (25%) of the usual dose. When the CYP3A4 and/or CYP2D6 inhibitor is withdrawn from the combination therapy, the aripiprazole dose should be increased Dosing recommendation in patients taking aripiprazole concomitantly with strong CYP3A4 and CYP2D6 inhibitors:[see DRUG INTERACTIONS ]. (7.1)
Patients who may be receiving a combination of strong, moderate, and weak inhibitors of CYP3A4 and CYP2D6 (eg, a potent CYP3A4 inhibitor and a moderate CYP2D6 inhibitor or a moderate CYP3A4 inhibitor with a moderate CYP2D6 inhibitor), the dosing may be reduced to one-quarter (25%) of the usual dose initially and then adjusted to achieve a favorable clinical response. Dosing recommendation in patients taking aripiprazole concomitantly with strong, moderate, or weak inhibitors of CYP3A4 and CYP2D6:
The aripiprazole dose in PM patients should initially be reduced to one-half (50%) of the usual dose and then adjusted to achieve a favorable clinical response. The dose of aripiprazole for PM patients who are administered a strong CYP3A4 inhibitor should be reduced to one-quarter (25%) of the usual dose . Dosing recommendation in patients who are classified as CYP2D6 poor metabolizers (PM):[see CLINICAL PHARMACOLOGY ] (12.3)
When a potential CYP3A4 inducer such as carbamazepine is added to aripiprazole therapy, the aripiprazole dose should be doubled. Additional dose increases should be based on clinical evaluation. When the CYP3A4 inducer is withdrawn from the combination therapy, the aripiprazole dose should be reduced to 10 mg to 15 mg . Dosage adjustment for patients taking potential CYP3A4 inducers:[see DRUG INTERACTIONS ] (7.1)

2.7 Dosing of Oral Solution

The oral solution can be substituted for tablets on a mg-per-mg basis up to the 25 mg dose level. Patients receiving 30 mg tablets should receive 25 mg of the solution . [see CLINICAL PHARMACOLOGY ] (12.3)

2.8 Dosing of Orally Disintegrating Tablets

The dosing for ABILIFY Orally Disintegrating Tablets is the same as for the oral tablets . [see DOSAGE AND ADMINISTRATION , , , and ] (2.12.22.32.4)

3 DOSAGE FORMS AND STRENGTHS

ABILIFY (aripiprazole) Tablets are available as described in Table 2.®

Table 2: ABILIFY Tablet Presentations
Tablet Strength | Tablet Color/Shape | Tablet Markings
2 mg | green modified rectangle | “A-006” and “2”
5 mg | blue modified rectangle | “A-007” and “5”
10 mg | pink modified rectangle | “A-008” and “10”
15 mg | yellow round | “A-009” and “15”
20 mg | white round | “A-010” and “20”
30 mg | pink round | “A-011” and “30”

ABILIFY DISCMELT (aripiprazole) Orally Disintegrating Tablets are available as described in Table 3.®

Table 3: ABILIFY DISCMELT Orally Disintegrating Tablet Presentations
Tablet Strength | Tablet Color/Shape | Tablet Markings
10 mg | pink (with scattered specks) round | “A” and “640” “10”
15 mg | yellow (with scattered specks) round | “A” and “641” “15”

ABILIFY (aripiprazole) Oral Solution (1 mg/mL) is a clear, colorless to light-yellow solution, supplied in child-resistant bottles along with a calibrated oral dosing cup.®

ABILIFY (aripiprazole) Injection for Intramuscular Use is a clear, colorless solution available as a ready-to-use, 9.75 mg/1.3 mL (7.5 mg/mL) solution in clear, Type 1 glass vials.®

4 CONTRAINDICATIONS

Known hypersensitivity reaction to ABILIFY. Reactions have ranged from pruritus/urticaria to anaphylaxis . [see ADVERSE REACTIONS ] (6.3)

5 WARNINGS AND PRECAUTIONS

5.1 Use in Elderly Patients with Dementia-Related Psychosis

Increased Mortality

Elderly patients with dementia-related psychosis treated with antipsychotic drugs are at an increased risk of death. ABILIFY (aripiprazole) is not approved for the treatment of patients with dementia-related psychosis . [see ] BOXED WARNING

Cerebrovascular Adverse Events, Including Stroke

In placebo-controlled clinical studies (two flexible dose and one fixed dose study) of dementia-related psychosis, there was an increased incidence of cerebrovascular adverse events (eg, stroke, transient ischemic attack), including fatalities, in aripiprazole-treated patients (mean age: 84 years; range: 78-88 years). In the fixed-dose study, there was a statistically significant dose response relationship for cerebrovascular adverse events in patients treated with aripiprazole. Aripiprazole is not approved for the treatment of patients with dementia-related psychosis . [see also ] BOXED WARNING

Safety Experience in Elderly Patients with Psychosis Associated with Alzheimer's Disease

In three, 10-week, placebo-controlled studies of aripiprazole in elderly patients with psychosis associated with Alzheimer's disease (n=938; mean age: 82.4 years; range: 56-99 years), the treatment-emergent adverse events that were reported at an incidence of ≥3% and aripiprazole incidence at least twice that for placebo were lethargy [placebo 2%, aripiprazole 5%], somnolence (including sedation) [placebo 3%, aripiprazole 8%], and incontinence (primarily, urinary incontinence) [placebo 1%, aripiprazole 5%], excessive salivation [placebo 0%, aripiprazole 4%], and lightheadedness [placebo 1%, aripiprazole 4%].

The safety and efficacy of ABILIFY in the treatment of patients with psychosis associated with dementia have not been established. If the prescriber elects to treat such patients with ABILIFY, vigilance should be exercised, particularly for the emergence of difficulty swallowing or excessive somnolence, which could predispose to accidental injury or aspiration . [see also ] BOXED WARNING

5.2 Suicidal Thoughts and Behaviors in Adolescents and Young Adults

Patients with major depressive disorder (MDD), both adult and pediatric, may experience worsening of their depression and/or the emergence of suicidal ideation and behavior (suicidality) or unusual changes in behavior, whether or not they are taking antidepressant medications, and this risk may persist until significant remission occurs. Suicide is a known risk of depression and certain other psychiatric disorders, and these disorders themselves are the strongest predictors of suicide. There has been a long-standing concern, however, that antidepressants may have a role in inducing worsening of depression and the emergence of suicidality in certain patients during the early phases of treatment. Pooled analyses of short-term, placebo-controlled trials of antidepressant drugs (SSRIs and others) showed that these drugs increase the risk of suicidal thinking and behavior (suicidality) in children, adolescents, and young adults (ages 18-24) with MDD and other psychiatric disorders. Short-term studies did not show an increase in the risk of suicidality with antidepressants compared to placebo in adults beyond age 24; there was a reduction with antidepressants compared to placebo in adults aged 65 and older.

The pooled analyses of placebo-controlled trials in children and adolescents with MDD, Obsessive Compulsive Disorder (OCD), or other psychiatric disorders included a total of 24 short-term trials of 9 antidepressant drugs in over 4400 patients. The pooled analyses of placebo-controlled trials in adults with MDD or other psychiatric disorders included a total of 295 short-term trials (median duration of 2 months) of 11 antidepressant drugs in over 77,000 patients. There was considerable variation in risk of suicidality among drugs, but a tendency toward an increase in the younger patients for almost all drugs studied. There were differences in absolute risk of suicidality across the different indications, with the highest incidence in MDD. The risk differences (drug vs. placebo), however, were relatively stable within age strata and across indications. These risk differences (drug-placebo difference in the number of cases of suicidality per 1000 patients treated) are provided in Table 4.

Table 4:
Age Range | Drug-Placebo Difference in Number of Cases of Suicidality per 1000 Patients Treated
 | Increases Compared to Placebo
<18 | 14 additional cases
18-24 | 5 additional cases
 | Decreases Compared to Placebo
25-64 | 1 fewer case
≥65 | 6 fewer cases

No suicides occurred in any of the pediatric trials. There were suicides in the adult trials, but the number was not sufficient to reach any conclusion about drug effect on suicide.

It is unknown whether the suicidality risk extends to longer-term use, ie, beyond several months. However, there is substantial evidence from placebo-controlled maintenance trials in adults with depression that the use of antidepressants can delay the recurrence of depression.

All patients being treated with antidepressants for any indication should be monitored appropriately and observed closely for clinical worsening, suicidality, and unusual changes in behavior, especially during the initial few months of a course of drug therapy, or at times of dose changes, either increases or decreases.

The following symptoms, anxiety, agitation, panic attacks, insomnia, irritability, hostility, aggressiveness, impulsivity, akathisia (psychomotor restlessness), hypomania, and mania, have been reported in adult and pediatric patients being treated with antidepressants for MDD as well as for other indications, both psychiatric and nonpsychiatric. Although a causal link between the emergence of such symptoms and either the worsening of depression and/or the emergence of suicidal impulses has not been established, there is concern that such symptoms may represent precursors to emerging suicidality.

Consideration should be given to changing the therapeutic regimen, including possibly discontinuing the medication, in patients whose depression is persistently worse, or who are experiencing emergent suicidality or symptoms that might be precursors to worsening depression or suicidality, especially if these symptoms are severe, abrupt in onset, or were not part of the patient’s presenting symptoms.

Prescriptions for ABILIFY should be written for the smallest quantity of tablets consistent with good patient management, in order to reduce the risk of overdose. Families and caregivers of patients being treated with antidepressants for major depressive disorder or other indications, both psychiatric and nonpsychiatric, should be alerted about the need to monitor patients for the emergence of agitation, irritability, unusual changes in behavior, and the other symptoms described above, as well as the emergence of suicidality, and to report such symptoms immediately to healthcare providers. Such monitoring should include daily observation by families and caregivers.

A major depressive episode may be the initial presentation of bipolar disorder. It is generally believed (though not established in controlled trials) that treating such an episode with an antidepressant alone may increase the likelihood of precipitation of a mixed/manic episode in patients at risk for bipolar disorder. Whether any of the symptoms described above represent such a conversion is unknown. However, prior to initiating treatment with an antidepressant, patients with depressive symptoms should be adequately screened to determine if they are at risk for bipolar disorder; such screening should include a detailed psychiatric history, including a family history of suicide, bipolar disorder, and depression. Screening Patients for Bipolar Disorder:

It should be noted that ABILIFY is not approved for use in treating depression in the pediatric population.

5.3 Neuroleptic Malignant Syndrome (NMS)

A potentially fatal symptom complex sometimes referred to as Neuroleptic Malignant Syndrome (NMS) may occur with administration of antipsychotic drugs, including aripiprazole. Rare cases of NMS occurred during aripiprazole treatment in the worldwide clinical database. Clinical manifestations of NMS are hyperpyrexia, muscle rigidity, altered mental status, and evidence of autonomic instability (irregular pulse or blood pressure, tachycardia, diaphoresis, and cardiac dysrhythmia). Additional signs may include elevated creatine phosphokinase, myoglobinuria (rhabdomyolysis), and acute renal failure.

The diagnostic evaluation of patients with this syndrome is complicated. In arriving at a diagnosis, it is important to exclude cases where the clinical presentation includes both serious medical illness (eg, pneumonia, systemic infection) and untreated or inadequately treated extrapyramidal signs and symptoms (EPS). Other important considerations in the differential diagnosis include central anticholinergic toxicity, heat stroke, drug fever, and primary central nervous system pathology.

The management of NMS should include: 1) immediate discontinuation of antipsychotic drugs and other drugs not essential to concurrent therapy; 2) intensive symptomatic treatment and medical monitoring; and 3) treatment of any concomitant serious medical problems for which specific treatments are available. There is no general agreement about specific pharmacological treatment regimens for uncomplicated NMS.

If a patient requires antipsychotic drug treatment after recovery from NMS, the potential reintroduction of drug therapy should be carefully considered. The patient should be carefully monitored, since recurrences of NMS have been reported.

5.4 Tardive Dyskinesia

A syndrome of potentially irreversible, involuntary, dyskinetic movements may develop in patients treated with antipsychotic drugs. Although the prevalence of the syndrome appears to be highest among the elderly, especially elderly women, it is impossible to rely upon prevalence estimates to predict, at the inception of antipsychotic treatment, which patients are likely to develop the syndrome. Whether antipsychotic drug products differ in their potential to cause tardive dyskinesia is unknown.

The risk of developing tardive dyskinesia and the likelihood that it will become irreversible are believed to increase as the duration of treatment and the total cumulative dose of antipsychotic drugs administered to the patient increase. However, the syndrome can develop, although much less commonly, after relatively brief treatment periods at low doses.

There is no known treatment for established cases of tardive dyskinesia, although the syndrome may remit, partially or completely, if antipsychotic treatment is withdrawn. Antipsychotic treatment, itself, however, may suppress (or partially suppress) the signs and symptoms of the syndrome and, thereby, may possibly mask the underlying process. The effect that symptomatic suppression has upon the long-term course of the syndrome is unknown.

Given these considerations, ABILIFY should be prescribed in a manner that is most likely to minimize the occurrence of tardive dyskinesia. Chronic antipsychotic treatment should generally be reserved for patients who suffer from a chronic illness that (1) is known to respond to antipsychotic drugs and (2) for whom alternative, equally effective, but potentially less harmful treatments are not available or appropriate. In patients who do require chronic treatment, the smallest dose and the shortest duration of treatment producing a satisfactory clinical response should be sought. The need for continued treatment should be reassessed periodically.

If signs and symptoms of tardive dyskinesia appear in a patient on ABILIFY, drug discontinuation should be considered. However, some patients may require treatment with ABILIFY despite the presence of the syndrome.

5.5 Metabolic Changes

Atypical antipsychotic drugs have been associated with metabolic changes that include hyperglycemia/diabetes mellitus, dyslipidemia, and body weight gain. While all drugs in the class have been shown to produce some metabolic changes, each drug has its own specific risk profile.

Hyperglycemia/Diabetes Mellitus

Hyperglycemia, in some cases extreme and associated with ketoacidosis or hyperosmolar coma or death, has been reported in patients treated with atypical antipsychotics. There have been reports of hyperglycemia in patients treated with ABILIFY . Assessment of the relationship between atypical antipsychotic use and glucose abnormalities is complicated by the possibility of an increased background risk of diabetes mellitus in patients with schizophrenia and the increasing incidence of diabetes mellitus in the general population. Given these confounders, the relationship between atypical antipsychotic use and hyperglycemia-related adverse events is not completely understood. However, epidemiological studies suggest an increased risk of treatment-emergent hyperglycemia-related adverse events in patients treated with the atypical antipsychotics. Because ABILIFY was not marketed at the time these studies were performed, it is not known if ABILIFY is associated with this increased risk. Precise risk estimates for hyperglycemia-related adverse events in patients treated with atypical antipsychotics are not available. [see ADVERSE REACTIONS , ] (6.26.3)

Patients with an established diagnosis of diabetes mellitus who are started on atypical antipsychotics should be monitored regularly for worsening of glucose control. Patients with risk factors for diabetes mellitus (eg, obesity, family history of diabetes) who are starting treatment with atypical antipsychotics should undergo fasting blood glucose testing at the beginning of treatment and periodically during treatment. Any patient treated with atypical antipsychotics should be monitored for symptoms of hyperglycemia including polydipsia, polyuria, polyphagia, and weakness. Patients who develop symptoms of hyperglycemia during treatment with atypical antipsychotics should undergo fasting blood glucose testing. In some cases, hyperglycemia has resolved when the atypical antipsychotic was discontinued; however, some patients required continuation of anti-diabetic treatment despite discontinuation of the suspect drug.

Adults

In an analysis of 13 placebo-controlled monotherapy trials in adults, primarily with schizophrenia or bipolar disorder, the mean change in fasting glucose in aripiprazole-treated patients (+4.4 mg/dL; median exposure 25 days; N=1057) was not significantly different than in placebo-treated patients (+2.5 mg/dL; median exposure 22 days; N=799). Table 5 shows the proportion of aripiprazole-treated patients with normal and borderline fasting glucose at baseline (median exposure 25 days) that had treatment-emergent high fasting glucose measurements compared to placebo-treated patients (median exposure 22 days).

Table 5: Changes in Fasting Glucose From Placebo-Controlled Monotherapy Trials in Adult Patients

 | Category Change (at least once) from Baseline | Treatment Arm | n/N | %
Fasting Glucose | Normal to High (<100 mg/dL to ≥126 mg/dL) | Aripiprazole | 31/822 | 3.8
Fasting Glucose | Normal to High (<100 mg/dL to ≥126 mg/dL) | Placebo | 22/605 | 3.6
Fasting Glucose | Borderline to High (≥100 mg/dL and <126 mg/dL to ≥126 mg/dL) | Aripiprazole | 31/176 | 17.6
Fasting Glucose | Borderline to High (≥100 mg/dL and <126 mg/dL to ≥126 mg/dL) | Placebo | 13/142 | 9.2

At 24 weeks, the mean change in fasting glucose in aripiprazole-treated patients was not significantly different than in placebo-treated patients [+2.2 mg/dL (n=42) and +9.6 mg/dL (n=28), respectively].

The mean change in fasting glucose in adjunctive aripiprazole-treated patients with major depressive disorder (+0.7 mg/dL; median exposure 42 days; N=241) was not significantly different than in placebo-treated patients (+0.8 mg/dL; median exposure 42 days; N=246). Table 6 shows the proportion of adult patients with changes in fasting glucose levels from two placebo-controlled, adjunctive trials (median exposure 42 days) in patients with major depressive disorder.

Table 6: Changes in Fasting Glucose From Placebo-Controlled Adjunctive Trials in Adult Patients with Major Depressive Disorder

 | Category Change (at least once) from Baseline | Treatment Arm | n/N | %
Fasting Glucose | Normal to High (<100 mg/dL to ≥126 mg/dL) | Aripiprazole | 2/201 | 1.0
Fasting Glucose | Normal to High (<100 mg/dL to ≥126 mg/dL) | Placebo | 2/204 | 1.0
Fasting Glucose | Borderline to High (≥100 mg/dL and <126 mg/dL to ≥126 mg/dL) | Aripiprazole | 4/34 | 11.8
Fasting Glucose | Borderline to High (≥100 mg/dL and <126 mg/dL to ≥126 mg/dL) | Placebo | 3/37 | 8.1

Pediatric Patients and Adolescents

In an analysis of two placebo-controlled trials in adolescents with schizophrenia (13 to 17 years) and pediatric patients with bipolar disorder (10 to 17 years), the mean change in fasting glucose in aripiprazole-treated patients (+4.8 mg/dL; with a median exposure of 43 days; N=259) was not significantly different than in placebo-treated patients (+1.7 mg/dL; with a median exposure of 42 days; N=123).

In an analysis of two placebo-controlled trials in pediatric and adolescent patients with irritability associated with autistic disorder (6 to 17 years) with median exposure of 56 days, the mean change in fasting glucose in aripiprazole-treated patients (–0.2 mg/dL; N=83) was not significantly different than in placebo-treated patients (–0.6 mg/dL; N=33). Table 7 shows the proportion of patients with changes in fasting glucose levels from the pooled adolescent schizophrenia and pediatric bipolar patients (median exposure of 42-43 days) as well as from two placebo-controlled trials in pediatric patients (6 to 17 years) with irritability associated with autistic disorder (median exposure of 56 days).

Table 7: Changes in Fasting Glucose From Placebo-Controlled Trials in Pediatric and Adolescent Patients

Category Change (at least once) from Baseline | Indication | Treatment Arm | n/N | %
Normal to High (<100 mg/dL to ≥126 mg/dL) Fasting Glucose
Normal to High (<100 mg/dL to ≥126 mg/dL) Fasting Glucose | Pooled Schizophrenia and Bipolar Disorder | Aripiprazole | 2/236 | 0.8
Normal to High (<100 mg/dL to ≥126 mg/dL) Fasting Glucose | Pooled Schizophrenia and Bipolar Disorder | Placebo | 2/110 | 1.8
Normal to High (<100 mg/dL to ≥126 mg/dL) Fasting Glucose | Irritability Associated with Autistic Disorder | Aripiprazole | 0/73 | 0
Normal to High (<100 mg/dL to ≥126 mg/dL) Fasting Glucose | Irritability Associated with Autistic Disorder | Placebo | 0/32 | 0
Borderline to High (≥100 mg/dL and <126 mg/dL to ≥126 mg/dL) Fasting Glucose
Borderline to High (≥100 mg/dL and <126 mg/dL to ≥126 mg/dL) Fasting Glucose | Pooled Schizophrenia and Bipolar Disorder | Aripiprazole | 1/22 | 4.5
Borderline to High (≥100 mg/dL and <126 mg/dL to ≥126 mg/dL) Fasting Glucose | Pooled Schizophrenia and Bipolar Disorder | Placebo | 0/12 | 0
Borderline to High (≥100 mg/dL and <126 mg/dL to ≥126 mg/dL) Fasting Glucose | Irritability Associated with Autistic Disorder | Aripiprazole | 0/9 | 0
Borderline to High (≥100 mg/dL and <126 mg/dL to ≥126 mg/dL) Fasting Glucose | Irritability Associated with Autistic Disorder | Placebo | 0/1 | 0

At 12 weeks in the pooled adolescent schizophrenia and pediatric bipolar disorder trials, the mean change in fasting glucose in aripiprazole-treated patients was not significantly different than in placebo-treated patients [+2.4 mg/dL (n=81) and +0.1 mg/dL (n=15), respectively].

Dyslipidemia

Undesirable alterations in lipids have been observed in patients treated with atypical antipsychotics.

There were no significant differences between aripiprazole- and placebo-treated patients in the proportion with changes from normal to clinically significant levels for fasting/nonfasting total cholesterol, fasting triglycerides, fasting LDLs, and fasting/nonfasting HDLs. Analyses of patients with at least 12 or 24 weeks of exposure were limited by small numbers of patients.

Adults

Table 8 shows the proportion of adult patients, primarily from pooled schizophrenia and bipolar disorder monotherapy placebo-controlled trials, with changes in total cholesterol (pooled from 17 trials; median exposure 21 to 25 days), fasting triglycerides (pooled from eight trials; median exposure 42 days), fasting LDL cholesterol (pooled from eight trials; median exposure 39 to 45 days, except for placebo-treated patients with baseline normal fasting LDL measurements, who had median treatment exposure of 24 days) and HDL cholesterol (pooled from nine trials; median exposure 40 to 42 days).

Table 8: Changes in Blood Lipid Parameters From Placebo-Controlled Monotherapy Trials in Adults

 | Treatment Arm | n/N | %
Normal to High (<200 mg/dL to ≥240 mg/dL) Total Cholesterol
Normal to High (<200 mg/dL to ≥240 mg/dL) Total Cholesterol | Aripiprazole | 34/1357 | 2.5
Normal to High (<200 mg/dL to ≥240 mg/dL) Total Cholesterol | Placebo | 27/973 | 2.8
Normal to High (<150 mg/dL to ≥200 mg/dL) Fasting Triglycerides
Normal to High (<150 mg/dL to ≥200 mg/dL) Fasting Triglycerides | Aripiprazole | 40/539 | 7.4
Normal to High (<150 mg/dL to ≥200 mg/dL) Fasting Triglycerides | Placebo | 30/431 | 7.0
Normal to High (<100 mg/dL to ≥160 mg/dL) Fasting LDL Cholesterol
Normal to High (<100 mg/dL to ≥160 mg/dL) Fasting LDL Cholesterol | Aripiprazole | 2/332 | 0.6
Normal to High (<100 mg/dL to ≥160 mg/dL) Fasting LDL Cholesterol | Placebo | 2/268 | 0.7
Normal to Low (≥40 mg/dL to <40 mg/dL) HDL Cholesterol
Normal to Low (≥40 mg/dL to <40 mg/dL) HDL Cholesterol | Aripiprazole | 121/1066 | 11.4
Normal to Low (≥40 mg/dL to <40 mg/dL) HDL Cholesterol | Placebo | 99/794 | 12.5

In monotherapy trials in adults, the proportion of patients at 12 weeks and 24 weeks with changes from Normal to High in total cholesterol (fasting/nonfasting), fasting triglycerides, and fasting LDL cholesterol were similar between aripiprazole- and placebo-treated patients: at 12 weeks, Total Cholesterol (fasting/nonfasting), 1/71 (1.4%) vs. 3/74 (4.1%); Fasting Triglycerides, 8/62 (12.9%) vs. 5/37 (13.5%); Fasting LDL Cholesterol, 0/34 (0%) vs. 1/25 (4.0%), respectively; and at 24 weeks, Total Cholesterol (fasting/nonfasting), 1/42 (2.4%) vs. 3/37 (8.1%); Fasting Triglycerides, 5/34 (14.7%) vs. 5/20 (25%); Fasting LDL Cholesterol, 0/22 (0%) vs. 1/18 (5.6%), respectively.

Table 9 shows the proportion of patients with changes in total cholesterol (fasting/nonfasting), fasting triglycerides, fasting LDL cholesterol, and HDL cholesterol from two placebo-controlled adjunctive trials in adult patients with major depressive disorder (median exposure 42 days).

Table 9: Changes in Blood Lipid Parameters From Placebo-Controlled Adjunctive Trials in Adult Patients with Major Depressive Disorder

 | Treatment Arm | n/N | %
Normal to High (<200 mg/dL to ≥240 mg/dL) Total Cholesterol
Normal to High (<200 mg/dL to ≥240 mg/dL) Total Cholesterol | Aripiprazole | 3/139 | 2.2
Normal to High (<200 mg/dL to ≥240 mg/dL) Total Cholesterol | Placebo | 7/135 | 5.2
Normal to High (<150 mg/dL to ≥200 mg/dL) Fasting Triglycerides
Normal to High (<150 mg/dL to ≥200 mg/dL) Fasting Triglycerides | Aripiprazole | 14/145 | 9.7
Normal to High (<150 mg/dL to ≥200 mg/dL) Fasting Triglycerides | Placebo | 6/147 | 4.1
Normal to High (<100 mg/dL to ≥160 mg/dL) Fasting LDL Cholesterol
Normal to High (<100 mg/dL to ≥160 mg/dL) Fasting LDL Cholesterol | Aripiprazole | 0/54 | 0
Normal to High (<100 mg/dL to ≥160 mg/dL) Fasting LDL Cholesterol | Placebo | 0/73 | 0
Normal to Low (≥40 mg/dL to <40 mg/dL) HDL Cholesterol
Normal to Low (≥40 mg/dL to <40 mg/dL) HDL Cholesterol | Aripiprazole | 17/318 | 5.3
Normal to Low (≥40 mg/dL to <40 mg/dL) HDL Cholesterol | Placebo | 10/286 | 3.5

Pediatric Patients and Adolescents

Table 10 shows the proportion of adolescents with schizophrenia (13 to 17 years) and pediatric patients with bipolar disorder (10 to 17 years) with changes in total cholesterol and HDL cholesterol (pooled from two placebo-controlled trials; median exposure 42 to 43 days) and fasting triglycerides (pooled from two placebo-controlled trials; median exposure 42 to 44 days).

Table 10: Changes in Blood Lipid Parameters From Placebo-Controlled Monotherapy Trials in Pediatric and Adolescent Patients

 | Treatment Arm | n/N | %
Normal to High (<170 mg/dL to ≥200 mg/dL) Total Cholesterol
Normal to High (<170 mg/dL to ≥200 mg/dL) Total Cholesterol | Aripiprazole | 3/220 | 1.4
Normal to High (<170 mg/dL to ≥200 mg/dL) Total Cholesterol | Placebo | 0/116 | 0
Normal to High (<150 mg/dL to ≥200 mg/dL) Fasting Triglycerides
Normal to High (<150 mg/dL to ≥200 mg/dL) Fasting Triglycerides | Aripiprazole | 7/187 | 3.7
Normal to High (<150 mg/dL to ≥200 mg/dL) Fasting Triglycerides | Placebo | 4/85 | 4.7
Normal to Low (≥40 mg/dL to <40 mg/dL) HDL Cholesterol
Normal to Low (≥40 mg/dL to <40 mg/dL) HDL Cholesterol | Aripiprazole | 27/236 | 11.4
Normal to Low (≥40 mg/dL to <40 mg/dL) HDL Cholesterol | Placebo | 22/109 | 20.2

In monotherapy trials of adolescents with schizophrenia and pediatric patients with bipolar disorder, the proportion of patients at 12 weeks and 24 weeks with changes from Normal to High in total cholesterol (fasting/nonfasting), fasting triglycerides, and fasting LDL cholesterol were similar between aripiprazole- and placebo-treated patients: at 12 weeks, Total Cholesterol (fasting/nonfasting), 0/57 (0%) vs. 0/15 (0%); Fasting Triglycerides, 2/72 (2.8%) vs. 1/14 (7.1%), respectively; and at 24 weeks, Total Cholesterol (fasting/nonfasting), 0/36 (0%) vs. 0/12 (0%); Fasting Triglycerides, 1/47 (2.1%) vs. 1/10 (10.0%), respectively.

Table 11 shows the proportion of patients with changes in total cholesterol (fasting/nonfasting) and fasting triglycerides (median exposure 56 days) and HDL cholesterol (median exposure 55 to 56 days) from two placebo-controlled trials in pediatric patients (6 to 17 years) with irritability associated with autistic disorder.

Table 11: Changes in Blood Lipid Parameters From Placebo-Controlled Trials in Pediatric Patients with Autistic Disorder

 | Treatment Arm | n/N | %
Normal to High (<170 mg/dL to ≥200 mg/dL) Total Cholesterol
Normal to High (<170 mg/dL to ≥200 mg/dL) Total Cholesterol | Aripiprazole | 1/95 | 1.1
Normal to High (<170 mg/dL to ≥200 mg/dL) Total Cholesterol | Placebo | 0/34 | 0
Normal to High (<150 mg/dL to ≥200 mg/dL) Fasting Triglycerides
Normal to High (<150 mg/dL to ≥200 mg/dL) Fasting Triglycerides | Aripiprazole | 0/75 | 0
Normal to High (<150 mg/dL to ≥200 mg/dL) Fasting Triglycerides | Placebo | 0/30 | 0
Normal to Low (≥40 mg/dL to <40 mg/dL) HDL Cholesterol
Normal to Low (≥40 mg/dL to <40 mg/dL) HDL Cholesterol | Aripiprazole | 9/107 | 8.4
Normal to Low (≥40 mg/dL to <40 mg/dL) HDL Cholesterol | Placebo | 5/49 | 10.2

Weight Gain

Weight gain has been observed with atypical antipsychotic use. Clinical monitoring of weight is recommended.

Adults

In an analysis of 13 placebo-controlled monotherapy trials, primarily from pooled schizophrenia and bipolar disorder, with a median exposure of 21 to 25 days, the mean change in body weight in aripiprazole-treated patients was +0.3 kg (N=1673) compared to –0.1 kg (N=1100) in placebo-controlled patients. At 24 weeks, the mean change from baseline in body weight in aripiprazole-treated patients was –1.5 kg (n=73) compared to –0.2 kg (n=46) in placebo-treated patients.

In the trials adding aripiprazole to antidepressants, patients first received 8 weeks of antidepressant treatment followed by 6 weeks of adjunctive aripiprazole or placebo in addition to their ongoing antidepressant treatment. The mean change in body weight in patients receiving adjunctive aripiprazole was +1.7 kg (N=347) compared to +0.4 kg (N=330) in patients receiving adjunctive placebo.

Table 12 shows the percentage of adult patients with weight gain ≥7% of body weight by indication.

Table 12: Percentage of Patients From Placebo-Controlled Trials in Adult Patients with Weight Gain ≥7% of Body Weight

 | Indication | Treatment Arm | N | Patients n (%)
Weight gain ≥7% of body weight
Weight gain ≥7% of body weight | Schizophreniaa | Aripiprazole | 852 | 69 (8.1)
Weight gain ≥7% of body weight | Schizophreniaa | Placebo | 379 | 12 (3.2)
Weight gain ≥7% of body weight | Bipolar Maniab | Aripiprazole | 719 | 16 (2.2)
Weight gain ≥7% of body weight | Bipolar Maniab | Placebo | 598 | 16 (2.7)
Weight gain ≥7% of body weight | Major Depressive Disorder (Adjunctive Therapy)c | Aripiprazole | 347 | 18 (5.2)
Weight gain ≥7% of body weight | Major Depressive Disorder (Adjunctive Therapy)c | Placebo | 330 | 2 (0.6)

4-6 weeks duration. 3 weeks duration. 6 weeks duration.abc

Pediatric Patients and Adolescents

In an analysis of two placebo-controlled trials in adolescents with schizophrenia (13 to 17 years) and pediatric patients with bipolar disorder (10 to 17 years) with median exposure of 42 to 43 days, the mean change in body weight in aripiprazole-treated patients was +1.6 kg (N=381) compared to +0.3 kg (N=187) in placebo-treated patients. At 24 weeks, the mean change from baseline in body weight in aripiprazole-treated patients was +5.8 kg (n=62) compared to +1.4 kg (n=13) in placebo-treated patients.

In two short-term, placebo-controlled trials in patients (6 to 17 years) with irritability associated with autistic disorder with median exposure of 56 days, the mean change in body weight in aripiprazole-treated patients was +1.6 kg (n=209) compared to +0.4 kg (n=98) in placebo-treated patients.

Table 13 shows the percentage of pediatric and adolescent patients with weight gain ≥7% of body weight by indication.

Table 13: Percentage of Patients From Placebo-Controlled Monotherapy Trials in Pediatric and Adolescent Patients with Weight Gain ≥7% of Body Weight

 | Indication | Treatment Arm | N | Patients n (%)
Weight gain ≥7%
of body weight
Weight gain ≥7% of body weight | Pooled Schizophrenia and Bipolar Mania a | Aripiprazole | 381 | 20 (5.2)
Weight gain ≥7% of body weight | Pooled Schizophrenia and Bipolar Mania a | Placebo | 187 | 3 (1.6)
Weight gain ≥7% of body weight | Irritability Associated with Autistic Disorder b | Aripiprazole | 209 | 55 (26.3)
Weight gain ≥7% of body weight | Irritability Associated with Autistic Disorder b | Placebo | 98 | 7 (7.1)

4-6 weeks duration. 8 weeks duration.ab

In an open-label trial that enrolled patients from the two placebo-controlled trials of adolescents with schizophrenia (13 to 17 years) and pediatric patients with bipolar disorder (10 to 17 years), 73.2% of patients (238/325) completed 26 weeks of therapy with ABILIFY. After 26 weeks, 32.8% of patients gained ≥7% of their body weight, not adjusted for normal growth. To adjust for normal growth, z-scores were derived (measured in standard deviations [SD]), which normalize for the natural growth of pediatric patients and adolescents by comparisons to age- and gender-matched population standards. A z-score change <0.5 SD is considered not clinically significant. After 26 weeks, the mean change in z-score was 0.09 SD.

In an open-label trial that enrolled patients from two short-term, placebo-controlled trials, patients (6 to 17 years) with irritability associated with autistic disorder, as well as patients, 60.3% (199/330) completed one year of therapy with ABILIFY. The mean change in weight z-score was 0.26 SDs for patients receiving >9 months of treatment. de novo

When treating pediatric patients for any indication, weight gain should be monitored and assessed against that expected for normal growth.

5.6 Orthostatic Hypotension

Aripiprazole may cause orthostatic hypotension, perhaps due to its α -adrenergic receptor antagonism. The incidence of orthostatic hypotension-associated events from short-term, placebo-controlled trials of adult patients on oral ABILIFY (n=2467) included (aripiprazole incidence, placebo incidence) orthostatic hypotension (1%, 0.3%), postural dizziness (0.5%, 0.3%), and syncope (0.5%, 0.4%); of pediatric patients 6 to 17 years of age (n=611) on oral ABILIFY included orthostatic hypotension (0.5%, 0%), postural dizziness (0.3%, 0%), and syncope (0.2%, 0%); and of patients on ABILIFY Injection (n=501) included orthostatic hypotension (0.6%, 0%), postural dizziness (0.2%, 0.5%), and syncope (0.4%, 0%).1

The incidence of a significant orthostatic change in blood pressure (defined as a decrease in systolic blood pressure ≥20 mmHg accompanied by an increase in heart rate ≥25 when comparing standing to supine values) for aripiprazole was not meaningfully different from placebo (aripiprazole incidence, placebo incidence): in adult oral aripiprazole-treated patients (4%, 2%), in pediatric oral aripiprazole-treated patients aged 6 to 17 years (0.2%, 1%), or in aripiprazole injection-treated patients (3%, 2%).

Aripiprazole should be used with caution in patients with known cardiovascular disease (history of myocardial infarction or ischemic heart disease, heart failure or conduction abnormalities), cerebrovascular disease, or conditions which would predispose patients to hypotension (dehydration, hypovolemia, and treatment with antihypertensive medications).

If parenteral benzodiazepine therapy is deemed necessary in addition to aripiprazole injection treatment, patients should be monitored for excessive sedation and for orthostatic hypotension . [see DRUG INTERACTIONS ] (7.3)

5.7 Leukopenia, Neutropenia, and Agranulocytosis

In clinical trial and/or postmarketing experience, events of leukopenia/neutropenia have been reported temporally related to antipsychotic agents, including ABILIFY. Agranulocytosis has also been reported. Class Effect:

Possible risk factors for leukopenia/neutropenia include pre-existing low white blood cell count (WBC) and history of drug-induced leukopenia/neutropenia. Patients with a history of a clinically significant low WBC or drug-induced leukopenia/neutropenia should have their complete blood count (CBC) monitored frequently during the first few months of therapy and discontinuation of ABILIFY should be considered at the first sign of a clinically significant decline in WBC in the absence of other causative factors.

Patients with clinically significant neutropenia should be carefully monitored for fever or other symptoms or signs of infection and treated promptly if such symptoms or signs occur. Patients with severe neutropenia (absolute neutrophil count <1000/mm) should discontinue ABILIFY and have their WBC followed until recovery.^3

5.8 Seizures/Convulsions

In short-term, placebo-controlled trials, seizures/convulsions occurred in 0.1% (3/2467) of adult patients treated with oral aripiprazole, in 0.2% (1/611) of pediatric patients (6 to 17 years), and in 0.2% (1/501) of adult aripiprazole injection-treated patients.

As with other antipsychotic drugs, aripiprazole should be used cautiously in patients with a history of seizures or with conditions that lower the seizure threshold, eg, Alzheimer's dementia. Conditions that lower the seizure threshold may be more prevalent in a population of 65 years or older.

5.9 Potential for Cognitive and Motor Impairment

ABILIFY, like other antipsychotics, may have the potential to impair judgment, thinking, or motor skills. For example, in short-term, placebo-controlled trials, somnolence (including sedation) was reported as follows (aripiprazole incidence, placebo incidence): in adult patients (n=2467) treated with oral ABILIFY (11%, 6%), in pediatric patients ages 6 to 17 (n=611) (24%, 6%), and in adult patients (n=501) on ABILIFY Injection (9%, 6%). Somnolence (including sedation) led to discontinuation in 0.3% (8/2467) of adult patients and 3% (15/611) of pediatric patients (6 to 17 years) on oral ABILIFY in short-term, placebo-controlled trials, but did not lead to discontinuation of any adult patients on ABILIFY Injection.

Despite the relatively modest increased incidence of these events compared to placebo, patients should be cautioned about operating hazardous machinery, including automobiles, until they are reasonably certain that therapy with ABILIFY does not affect them adversely.

5.10 Body Temperature Regulation

Disruption of the body's ability to reduce core body temperature has been attributed to antipsychotic agents. Appropriate care is advised when prescribing aripiprazole for patients who will be experiencing conditions which may contribute to an elevation in core body temperature, (eg, exercising strenuously, exposure to extreme heat, receiving concomitant medication with anticholinergic activity, or being subject to dehydration) . [see ADVERSE REACTIONS ] (6.3)

5.11 Suicide

The possibility of a suicide attempt is inherent in psychotic illnesses, bipolar disorder, and major depressive disorder, and close supervision of high-risk patients should accompany drug therapy. Prescriptions for ABILIFY should be written for the smallest quantity consistent with good patient management in order to reduce the risk of overdose . [see ADVERSE REACTIONS , ] (6.26.3)

In two 6-week, placebo-controlled studies of aripiprazole as adjunctive treatment of major depressive disorder, the incidences of suicidal ideation and suicide attempts were 0% (0/371) for aripiprazole and 0.5% (2/366) for placebo.

5.12 Dysphagia

Esophageal dysmotility and aspiration have been associated with antipsychotic drug use, including ABILIFY. Aspiration pneumonia is a common cause of morbidity and mortality in elderly patients, in particular those with advanced Alzheimer's dementia. Aripiprazole and other antipsychotic drugs should be used cautiously in patients at risk for aspiration pneumonia . [see WARNINGS AND PRECAUTIONS and ADVERSE REACTIONS ] (5.1) (6.3)

5.13 Use in Patients with Concomitant Illness

Clinical experience with ABILIFY in patients with certain concomitant systemic illnesses is limited . [see USE IN SPECIFIC POPULATIONS , ] (8.68.7)

ABILIFY has not been evaluated or used to any appreciable extent in patients with a recent history of myocardial infarction or unstable heart disease. Patients with these diagnoses were excluded from premarketing clinical studies . [see WARNINGS AND PRECAUTIONS , ] (5.15.6)

6 ADVERSE REACTIONS

6.1 Overall Adverse Reactions Profile

The following are discussed in more detail in other sections of the labeling:

- Use in Elderly Patients with Dementia-Related Psychosis [see BOXED WARNING and WARNINGS AND PRECAUTIONS ] (5.1)
- Suicidal Thoughts and Behaviors in Adolescents and Young Adults [see BOXED WARNING and WARNINGS AND PRECAUTIONS ] (5.2)
- Neuroleptic Malignant Syndrome (NMS) [see WARNINGS AND PRECAUTIONS ] (5.3)
- Tardive Dyskinesia [see WARNINGS AND PRECAUTIONS ] (5.4)
- Metabolic Changes [see WARNINGS AND PRECAUTIONS ] (5.5)
- Orthostatic Hypotension [see WARNINGS AND PRECAUTIONS ] (5.6)
- Leukopenia, Neutropenia, and Agranulocytosis [see WARNINGS AND PRECAUTIONS ] (5.7)
- Seizures/Convulsions [see WARNINGS AND PRECAUTIONS ] (5.8)
- Potential for Cognitive and Motor Impairment [see WARNINGS AND PRECAUTIONS ] (5.9)
- Body Temperature Regulation [see WARNINGS AND PRECAUTIONS ] (5.10)
- Suicide [see WARNINGS AND PRECAUTIONS ] (5.11)
- Dysphagia [see WARNINGS AND PRECAUTIONS ] (5.12)
- Use in Patients with Concomitant Illness [see WARNINGS AND PRECAUTIONS ] (5.13)

The most common adverse reactions in adult patients in clinical trials (≥10%) were nausea, vomiting, constipation, headache, dizziness, akathisia, anxiety, insomnia, and restlessness.

The most common adverse reactions in the pediatric clinical trials (≥10%) were somnolence, headache, vomiting, extrapyramidal disorder, fatigue, increased appetite, insomnia, nausea, nasopharyngitis, and weight increased.

Aripiprazole has been evaluated for safety in 13,543 adult patients who participated in multiple-dose, clinical trials in schizophrenia, bipolar disorder, major depressive disorder, Dementia of the Alzheimer’s type, Parkinson’s disease, and alcoholism, and who had approximately 7619 patient-years of exposure to oral aripiprazole and 749 patients with exposure to aripiprazole injection. A total of 3390 patients were treated with oral aripiprazole for at least 180 days and 1933 patients treated with oral aripiprazole had at least 1 year of exposure.

Aripiprazole has been evaluated for safety in 920 patients (6 to 17 years) who participated in multiple-dose, clinical trials in schizophrenia, bipolar mania, or autistic disorder and who had approximately 517 patient-years of exposure to oral aripiprazole. A total of 465 pediatric patients were treated with oral aripiprazole for at least 180 days and 117 pediatric patients treated with oral aripiprazole had at least 1 year of exposure.

The conditions and duration of treatment with aripiprazole (monotherapy and adjunctive therapy with antidepressants or mood stabilizers) included (in overlapping categories) double-blind, comparative and noncomparative open-label studies, inpatient and outpatient studies, fixed- and flexible-dose studies, and short- and longer-term exposure.

Adverse events during exposure were obtained by collecting volunteered adverse events, as well as results of physical examinations, vital signs, weights, laboratory analyses, and ECG. Adverse experiences were recorded by clinical investigators using terminology of their own choosing. In the tables and tabulations that follow, MedDRA dictionary terminology has been used to classify reported adverse events into a smaller number of standardized event categories, in order to provide a meaningful estimate of the proportion of individuals experiencing adverse events.

The stated frequencies of adverse reactions represent the proportion of individuals who experienced at least once, a treatment-emergent adverse event of the type listed. An event was considered treatment emergent if it occurred for the first time or worsened while receiving therapy following baseline evaluation. There was no attempt to use investigator causality assessments; ie, all events meeting the defined criteria, regardless of investigator causality, are included.

Throughout this section, adverse reactions are reported. These are adverse events that were considered to be reasonably associated with the use of ABILIFY (adverse drug reactions) based on the comprehensive assessment of the available adverse event information. A causal association for ABILIFY often cannot be reliably established in individual cases.

The figures in the tables and tabulations cannot be used to predict the incidence of side effects in the course of usual medical practice where patient characteristics and other factors differ from those that prevailed in the clinical trials. Similarly, the cited frequencies cannot be compared with figures obtained from other clinical investigations involving different treatment, uses, and investigators. The cited figures, however, do provide the prescriber with some basis for estimating the relative contribution of drug and nondrug factors to the adverse reaction incidence in the population studied.

6.2 Clinical Studies Experience

Adult Patients with Schizophrenia

The following findings are based on a pool of five placebo-controlled trials (four 4-week and one 6-week) in which oral aripiprazole was administered in doses ranging from 2 mg/day to 30 mg/day.

Adverse Reactions Associated with Discontinuation of Treatment

Overall, there was little difference in the incidence of discontinuation due to adverse reactions between aripiprazole-treated (7%) and placebo-treated (9%) patients. The types of adverse reactions that led to discontinuation were similar for the aripiprazole-treated and placebo-treated patients.

Commonly Observed Adverse Reactions

The only commonly observed adverse reaction associated with the use of aripiprazole in patients with schizophrenia (incidence of 5% or greater and aripiprazole incidence at least twice that for placebo) was akathisia (aripiprazole 8%; placebo 4%).

Adult Patients with Bipolar Mania

Monotherapy

The following findings are based on a pool of 3-week, placebo-controlled, bipolar mania trials in which oral aripiprazole was administered at doses of 15 mg/day or 30 mg/day.

Adverse Reactions Associated with Discontinuation of Treatment

Overall, in patients with bipolar mania, there was little difference in the incidence of discontinuation due to adverse reactions between aripiprazole-treated (11%) and placebo-treated (10%) patients. The types of adverse reactions that led to discontinuation were similar between the aripiprazole-treated and placebo-treated patients.

Commonly Observed Adverse Reactions

Commonly observed adverse reactions associated with the use of aripiprazole in patients with bipolar mania (incidence of 5% or greater and aripiprazole incidence at least twice that for placebo) are shown in Table 14.

Table 14: Commonly Observed Adverse Reactions in Short-Term, Placebo-Controlled Trials of Adult Patients with Bipolar Mania Treated with Oral ABILIFY Monotherapy
 | Percentage of Patients Reporting Reaction
Preferred Term | Aripiprazole (n=917) | Placebo (n=753)
Akathisia | 13 | 4
Sedation | 8 | 3
Restlessness | 6 | 3
Tremor | 6 | 3
Extrapyramidal Disorder | 5 | 2

Less Common Adverse Reactions in Adults

Table 15 enumerates the pooled incidence, rounded to the nearest percent, of adverse reactions that occurred during acute therapy (up to 6 weeks in schizophrenia and up to 3 weeks in bipolar mania), including only those reactions that occurred in 2% or more of patients treated with aripiprazole (doses ≥2 mg/day) and for which the incidence in patients treated with aripiprazole was greater than the incidence in patients treated with placebo in the combined dataset.

Table 15: Adverse Reactions in Short-Term, Placebo-Controlled Trials in Adult Patients Treated with Oral ABILIFY
 | Percentage of Patients Reporting Reactiona
System Organ Class Preferred Term | Aripiprazole (n=1843) | Placebo (n=1166)
Eye Disorders
Blurred Vision | 3 | 1
Gastrointestinal Disorders
Nausea | 15 | 11
Constipation | 11 | 7
Vomiting | 11 | 6
Dyspepsia | 9 | 7
Dry Mouth | 5 | 4
Toothache | 4 | 3
Abdominal Discomfort | 3 | 2
Stomach Discomfort | 3 | 2
General Disorders and Administration Site Conditions
Fatigue | 6 | 4
Pain | 3 | 2
Musculoskeletal and Connective Tissue Disorders
Musculoskeletal Stiffness | 4 | 3
Pain in Extremity | 4 | 2
Myalgia | 2 | 1
Muscle Spasms | 2 | 1
Nervous System Disorders
Headache | 27 | 23
Dizziness | 10 | 7
Akathisia | 10 | 4
Sedation | 7 | 4
Extrapyramidal Disorder | 5 | 3
Tremor | 5 | 3
Somnolence | 5 | 3
Psychiatric Disorders
Agitation | 19 | 17
Insomnia | 18 | 13
Anxiety | 17 | 13
Restlessness | 5 | 3
Respiratory, Thoracic, and Mediastinal Disorders
Pharyngolaryngeal Pain | 3 | 2
Cough | 3 | 2
Adverse reactions reported by at least 2% of patients treated with oral aripiprazole, except adverse reactions which had an incidence equal to or less than placebo.a

An examination of population subgroups did not reveal any clear evidence of differential adverse reaction incidence on the basis of age, gender, or race.

Adult Patients with Adjunctive Therapy with Bipolar Mania

The following findings are based on a placebo-controlled trial of adult patients with bipolar disorder in which aripiprazole was administered at doses of 15 mg/day or 30 mg/day as adjunctive therapy with lithium or valproate.

Adverse Reactions Associated with Discontinuation of Treatment

In a study of patients who were already tolerating either lithium or valproate as monotherapy, discontinuation rates due to adverse reactions were 12% for patients treated with adjunctive aripiprazole compared to 6% for patients treated with adjunctive placebo. The most common adverse drug reactions associated with discontinuation in the adjunctive aripiprazole-treated compared to placebo-treated patients were akathisia (5% and 1%, respectively) and tremor (2% and 1%, respectively).

Commonly Observed Adverse Reactions

The commonly observed adverse reactions associated with adjunctive aripiprazole and lithium or valproate in patients with bipolar mania (incidence of 5% or greater and incidence at least twice that for adjunctive placebo) were: akathisia, insomnia, and extrapyramidal disorder.

Less Common Adverse Reactions in Adult Patients with Adjunctive Therapy in Bipolar Mania

Table 16 enumerates the incidence, rounded to the nearest percent, of adverse reactions that occurred during acute treatment (up to 6 weeks), including only those reactions that occurred in 2% or more of patients treated with adjunctive aripiprazole (doses of 15 mg/day or 30 mg/day) and lithium or valproate and for which the incidence in patients treated with this combination was greater than the incidence in patients treated with placebo plus lithium or valproate.

Table 16: Adverse Reactions in a Short-Term, Placebo-Controlled Trial of Adjunctive Therapy in Patients with Bipolar Disorder
 | Percentage of Patients Reporting Reactiona
System Organ Class Preferred Term | Aripiprazole + Li or Val* (n=253) | Placebo + Li or Val* (n=130)
Gastrointestinal Disorders
Nausea | 8 | 5
Vomiting | 4 | 0
Salivary Hypersecretion | 4 | 2
Dry Mouth | 2 | 1
Infections and Infestations
Nasopharyngitis | 3 | 2
Investigations
Weight Increased | 2 | 1
Nervous System Disorders
Akathisia | 19 | 5
Tremor | 9 | 6
Extrapyramidal Disorder | 5 | 1
Dizziness | 4 | 1
Sedation | 4 | 2
Psychiatric Disorders
Insomnia | 8 | 4
Anxiety | 4 | 1
Restlessness | 2 | 1
Adverse reactions reported by at least 2% of patients treated with oral aripiprazole, except adverse reactions which had an incidence equal to or less than placebo. * Lithium or Valproatea

Pediatric Patients (13 to 17 years) with Schizophrenia

The following findings are based on one 6-week, placebo-controlled trial in which oral aripiprazole was administered in doses ranging from 2 mg/day to 30 mg/day.

Adverse Reactions Associated with Discontinuation of Treatment

The incidence of discontinuation due to adverse reactions between aripiprazole-treated and placebo-treated pediatric patients (13 to 17 years) was 5% and 2%, respectively.

Commonly Observed Adverse Reactions

Commonly observed adverse reactions associated with the use of aripiprazole in adolescent patients with schizophrenia (incidence of 5% or greater and aripiprazole incidence at least twice that for placebo) were extrapyramidal disorder, somnolence, and tremor.

Pediatric Patients (10 to 17 years) with Bipolar Mania

The following findings are based on one 4-week, placebo-controlled trial in which oral aripiprazole was administered in doses of 10 mg/day or 30 mg/day.

Adverse Reactions Associated with Discontinuation of Treatment

The incidence of discontinuation due to adverse reactions between aripiprazole-treated and placebo-treated pediatric patients (10 to 17 years) was 7% and 2%, respectively.

Commonly Observed Adverse Reactions

Commonly observed adverse reactions associated with the use of aripiprazole in pediatric patients with bipolar mania (incidence of 5% or greater and aripiprazole incidence at least twice that for placebo) are shown in Table 17.

Table 17: Commonly Observed Adverse Reactions in Short-Term, Placebo-Controlled Trials of Pediatric Patients (10 to 17 years) with Bipolar Mania Treated with Oral ABILIFY
 | Percentage of Patients Reporting Reaction
Preferred Term | Aripiprazole (n=197) | Placebo (n=97)
Somnolence | 23 | 3
Extrapyramidal Disorder | 20 | 3
Fatigue | 11 | 4
Nausea | 11 | 4
Akathisia | 10 | 2
Blurred Vision | 8 | 0
Salivary Hypersecretion | 6 | 0
Dizziness | 5 | 1

Pediatric Patients (6 to 17 years) with Autistic Disorder

The following findings are based on two 8-week, placebo-controlled trials in which oral aripiprazole was administered in doses of 2 mg/day to 15 mg/day.

Adverse Reactions Associated with Discontinuation of Treatment

The incidence of discontinuation due to adverse reactions between aripiprazole-treated and placebo-treated pediatric patients (6 to 17 years) was 10% and 8%, respectively.

Commonly Observed Adverse Reactions

Commonly observed adverse reactions associated with the use of aripiprazole in pediatric patients with autistic disorder (incidence of 5% or greater and aripiprazole incidence at least twice that for placebo) are shown in Table 18.

Table 18: Commonly Observed Adverse Reactions in Short-Term, Placebo-Controlled Trials of Pediatric Patients (6 to 17 years) with Autistic Disorder Treated with Oral ABILIFY
 | Percentage of Patients Reporting Reaction
Preferred Term | Aripiprazole (n=212) | Placebo (n=101)
Sedation | 21 | 4
Fatigue | 17 | 2
Vomiting | 14 | 7
Somnolence | 10 | 4
Tremor | 10 | 0
Pyrexia | 9 | 1
Drooling | 9 | 0
Decreased Appetite | 7 | 2
Salivary Hypersecretion | 6 | 1
Extrapyramidal Disorder | 6 | 0
Lethargy | 5 | 0

Less Common Adverse Reactions in Pediatric Patients (6 to 17 years) with Schizophrenia, Bipolar Mania, or Autistic Disorder

Table 19 enumerates the pooled incidence, rounded to the nearest percent, of adverse reactions that occurred during acute therapy (up to 6 weeks in schizophrenia, up to 4 weeks in bipolar mania, and up to 8 weeks in autistic disorder), including only those reactions that occurred in 1% or more of pediatric patients treated with aripiprazole (doses ≥2 mg/day) and for which the incidence in patients treated with aripiprazole was greater than the incidence in patients treated with placebo.

Table 19: Adverse Reactions in Short-Term, Placebo-Controlled Trials of Pediatric Patients (6 to 17 years) Treated with Oral ABILIFY
 | Percentage of Patients Reporting Reactiona
System Organ Class Preferred Term | Aripiprazole (n=611) | Placebo (n=298)
Eye Disorders
Blurred Vision | 3 | 0
Gastrointestinal Disorders
Vomiting | 9 | 7
Nausea | 8 | 4
Diarrhea | 5 | 3
Salivary Hypersecretion | 4 | 1
Abdominal Pain Upper | 3 | 2
Constipation | 3 | 2
Dry Mouth | 1 | 0
General Disorders and Administration Site Conditions
Fatigue | 10 | 2
Pyrexia | 5 | 1
Irritability | 1 | 0
Thirst | 1 | 0
Infections and Infestations
Nasopharyngitis | 6 | 3
Investigations
Weight Increased | 2 | 1
Metabolism and Nutrition Disorders
Increased Appetite | 7 | 3
Decreased Appetite | 4 | 2
Musculoskeletal and Connective Tissue Disorders
Arthralgia | 1 | 0
Musculoskeletal Stiffness | 1 | 0
Nervous System Disorders
Somnolence | 16 | 4
Extrapyramidal Disorder | 14 | 2
Headache | 13 | 12
Sedation | 8 | 1
Akathisia | 6 | 1
Tremor | 6 | 1
Drooling | 4 | 0
Dizziness | 3 | 1
Lethargy | 2 | 0
Dystonia | 1 | 0
Dyskinesia | 1 | 0
Hypersomnia | 1 | 0
Reproductive System and Breast Disorders
Dysmenorrhoea* | 2 | 1
Respiratory, Thoracic, and Mediastinal Disorders
Rhinorrhoea | 2 | 1
Skin and Subcutaneous Tissue Disorders
Rash | 2 | 1
Adverse reactions reported by at least 1% of pediatric patients treated with oral aripiprazole, except adverse reactions which had an incidence equal to or less than placebo.a
Adjusted for gender.*

Adult Patients Receiving ABILIFY as Adjunctive Treatment of Major Depressive Disorder

The following findings are based on a pool of two placebo-controlled trials of patients with major depressive disorder in which aripiprazole was administered at doses of 2 mg to 20 mg as adjunctive treatment to continued antidepressant therapy.

Adverse Reactions Associated with Discontinuation of Treatment

The incidence of discontinuation due to adverse reactions was 6% for adjunctive aripiprazole-treated patients and 2% for adjunctive placebo-treated patients.

Commonly Observed Adverse Reactions

The commonly observed adverse reactions associated with the use of adjunctive aripiprazole in patients with major depressive disorder (incidence of 5% or greater and aripiprazole incidence at least twice that for placebo) were: akathisia, restlessness, insomnia, constipation, fatigue, and blurred vision.

Less Common Adverse Reactions in Adult Patients with Major Depressive Disorder

Table 20 enumerates the pooled incidence, rounded to the nearest percent, of adverse reactions that occurred during acute therapy (up to 6 weeks), including only those adverse reactions that occurred in 2% or more of patients treated with adjunctive aripiprazole (doses ≥2 mg/day) and for which the incidence in patients treated with adjunctive aripiprazole was greater than the incidence in patients treated with adjunctive placebo in the combined dataset.

Table 20: Adverse Reactions in Short-Term, Placebo-Controlled Adjunctive Trials in Patients with Major Depressive Disorder
 | Percentage of Patients Reporting Reactiona
System Organ Class Preferred Term | Aripiprazole+ADT* (n=371) | Placebo+ADT* (n=366)
Eye Disorders
Blurred Vision | 6 | 1
Gastrointestinal Disorders
Constipation | 5 | 2
General Disorders and Administration Site Conditions
Fatigue | 8 | 4
Feeling Jittery | 3 | 1
Infections and Infestations
Upper Respiratory Tract Infection | 6 | 4
Investigations
Weight Increased | 3 | 2
Metabolism and Nutrition Disorders
Increased Appetite | 3 | 2
Musculoskeletal and Connective Tissue Disorders
Arthralgia | 4 | 3
Myalgia | 3 | 1
Nervous System Disorders
Akathisia | 25 | 4
Somnolence | 6 | 4
Tremor | 5 | 4
Sedation | 4 | 2
Dizziness | 4 | 2
Disturbance in Attention | 3 | 1
Extrapyramidal Disorder | 2 | 0
Psychiatric Disorders
Restlessness | 12 | 2
Insomnia | 8 | 2
Adverse reactions reported by at least 2% of patients treated with adjunctive aripiprazole, except adverse reactions which had an incidence equal to or less than placebo. * Antidepressant Therapya

Patients with Agitation Associated with Schizophrenia or Bipolar Mania (Intramuscular Injection)

The following findings are based on a pool of three placebo-controlled trials of patients with agitation associated with schizophrenia or bipolar mania in which aripiprazole injection was administered at doses of 5.25 mg to 15 mg.

Adverse Reactions Associated with Discontinuation of Treatment

Overall, in patients with agitation associated with schizophrenia or bipolar mania, there was little difference in the incidence of discontinuation due to adverse reactions between aripiprazole-treated (0.8%) and placebo-treated (0.5%) patients.

Commonly Observed Adverse Reactions

There was one commonly observed adverse reaction (nausea) associated with the use of aripiprazole injection in patients with agitation associated with schizophrenia and bipolar mania (incidence of 5% or greater and aripiprazole incidence at least twice that for placebo).

Less Common Adverse Reactions in Patients with Agitation Associated with Schizophrenia or Bipolar Mania

Table 21 enumerates the pooled incidence, rounded to the nearest percent, of adverse reactions that occurred during acute therapy (24-hour), including only those adverse reactions that occurred in 2% or more of patients treated with aripiprazole injection (doses ≥5.25 mg/day) and for which the incidence in patients treated with aripiprazole injection was greater than the incidence in patients treated with placebo in the combined dataset.

Table 21: Adverse Reactions in Short-Term, Placebo-Controlled Trials in Patients Treated with ABILIFY Injection
 | Percentage of Patients Reporting Reactiona
System Organ Class Preferred Term | Aripiprazole (n=501) | Placebo (n=220)
Cardiac Disorders
Tachycardia | 2 | <1
Gastrointestinal Disorders
Nausea | 9 | 3
Vomiting | 3 | 1
General Disorders and Administration Site Conditions
Fatigue | 2 | 1
Nervous System Disorders
Headache | 12 | 7
Dizziness | 8 | 5
Somnolence | 7 | 4
Sedation | 3 | 2
Akathisia | 2 | 0
Adverse reactions reported by at least 2% of patients treated with aripiprazole injection, except adverse reactions which had an incidence equal to or less than placebo.a

Dose-Related Adverse Reactions

Schizophrenia

Dose response relationships for the incidence of treatment-emergent adverse events were evaluated from four trials in adult patients with schizophrenia comparing various fixed doses (2 mg/day, 5 mg/day, 10 mg/day, 15 mg/day, 20 mg/day, and 30 mg/day) of oral aripiprazole to placebo. This analysis, stratified by study, indicated that the only adverse reaction to have a possible dose response relationship, and then most prominent only with 30 mg, was somnolence [including sedation]; (incidences were placebo, 7.1%; 10 mg, 8.5%; 15 mg, 8.7%; 20 mg, 7.5%; 30 mg, 12.6%).

In the study of pediatric patients (13 to 17 years of age) with schizophrenia, three common adverse reactions appeared to have a possible dose response relationship: extrapyramidal disorder (incidences were placebo, 5.0%; 10 mg, 13.0%; 30 mg, 21.6%); somnolence (incidences were placebo, 6.0%; 10 mg, 11.0%; 30 mg, 21.6%); and tremor (incidences were placebo, 2.0%; 10 mg, 2.0%; 30 mg, 11.8%).

Bipolar Mania

In the study of pediatric patients (10 to 17 years of age) with bipolar mania, four common adverse reactions had a possible dose response relationship at 4 weeks; extrapyramidal disorder (incidences were placebo, 3.1%; 10 mg, 12.2%; 30 mg, 27.3%); somnolence (incidences were placebo, 3.1%; 10 mg, 19.4%; 30 mg, 26.3%); akathisia (incidences were placebo, 2.1%; 10 mg, 8.2%; 30 mg, 11.1%); and salivary hypersecretion (incidences were placebo, 0%; 10 mg, 3.1%; 30 mg, 8.1%).

Autistic Disorder

In a study of pediatric patients (6 to 17 years of age) with autistic disorder, one common adverse reaction had a possible dose response relationship: fatigue (incidences were placebo, 0%; 5 mg, 3.8%; 10 mg, 22.0%; 15 mg, 18.5%).

Extrapyramidal Symptoms

Schizophrenia

In short-term, placebo-controlled trials in schizophrenia in adults, the incidence of reported EPS-related events, excluding events related to akathisia, for aripiprazole-treated patients was 13% vs. 12% for placebo; and the incidence of akathisia-related events for aripiprazole-treated patients was 8% vs. 4% for placebo. In the short-term, placebo-controlled trial of schizophrenia in pediatric patients (13 to 17 years), the incidence of reported EPS-related events, excluding events related to akathisia, for aripiprazole-treated patients was 25% vs. 7% for placebo; and the incidence of akathisia-related events for aripiprazole-treated patients was 9% vs. 6% for placebo.

Objectively collected data from those trials was collected on the Simpson Angus Rating Scale (for EPS), the Barnes Akathisia Scale (for akathisia), and the Assessments of Involuntary Movement Scales (for dyskinesias). In the adult schizophrenia trials, the objectively collected data did not show a difference between aripiprazole and placebo, with the exception of the Barnes Akathisia Scale (aripiprazole, 0.08; placebo, −0.05). In the pediatric (13 to 17 years) schizophrenia trial, the objectively collected data did not show a difference between aripiprazole and placebo, with the exception of the Simpson Angus Rating Scale (aripiprazole, 0.24; placebo, −0.29).

Similarly, in a long-term (26-week), placebo-controlled trial of schizophrenia in adults, objectively collected data on the Simpson Angus Rating Scale (for EPS), the Barnes Akathisia Scale (for akathisia), and the Assessments of Involuntary Movement Scales (for dyskinesias) did not show a difference between aripiprazole and placebo.

Bipolar Mania

In the short-term, placebo-controlled trials in bipolar mania in adults, the incidence of reported EPS-related events, excluding events related to akathisia, for monotherapy aripiprazole-treated patients was 16% vs. 8% for placebo and the incidence of akathisia-related events for monotherapy aripiprazole-treated patients was 13% vs. 4% for placebo. In the 6-week, placebo-controlled trial in bipolar mania for adjunctive therapy with lithium or valproate, the incidence of reported EPS-related events, excluding events related to akathisia for adjunctive aripiprazole-treated patients was 15% vs. 8% for adjunctive placebo and the incidence of akathisia-related events for adjunctive aripiprazole-treated patients was 19% vs. 5% for adjunctive placebo. In the short-term, placebo-controlled trial in bipolar mania in pediatric (10 to 17 years) patients, the incidence of reported EPS-related events, excluding events related to akathisia, for aripiprazole-treated patients was 26% vs. 5% for placebo and the incidence of akathisia-related events for aripiprazole-treated patients was 10% vs. 2% for placebo.

In the adult bipolar mania trials with monotherapy aripiprazole, the Simpson Angus Rating Scale and the Barnes Akathisia Scale showed a significant difference between aripiprazole and placebo (aripiprazole, 0.50; placebo, −0.01 and aripiprazole, 0.21; placebo, −0.05). Changes in the Assessments of Involuntary Movement Scales were similar for the aripiprazole and placebo groups. In the bipolar mania trials with aripiprazole as adjunctive therapy with either lithium or valproate, the Simpson Angus Rating Scale and the Barnes Akathisia Scale showed a significant difference between adjunctive aripiprazole and adjunctive placebo (aripiprazole, 0.73; placebo, 0.07 and aripiprazole, 0.30; placebo, 0.11). Changes in the Assessments of Involuntary Movement Scales were similar for adjunctive aripiprazole and adjunctive placebo. In the pediatric (10 to 17 years), short-term, bipolar mania trial, the Simpson Angus Rating Scale showed a significant difference between aripiprazole and placebo (aripiprazole, 0.90; placebo, –0.05). Changes in the Barnes Akathisia Scale and the Assessments of Involuntary Movement Scales were similar for the aripiprazole and placebo groups.

Major Depressive Disorder

In the short-term, placebo-controlled trials in major depressive disorder, the incidence of reported EPS-related events, excluding events related to akathisia, for adjunctive aripiprazole-treated patients was 8% vs. 5% for adjunctive placebo-treated patients; and the incidence of akathisia-related events for adjunctive aripiprazole-treated patients was 25% vs. 4% for adjunctive placebo-treated patients.

In the major depressive disorder trials, the Simpson Angus Rating Scale and the Barnes Akathisia Scale showed a significant difference between adjunctive aripiprazole and adjunctive placebo (aripiprazole, 0.31; placebo, 0.03 and aripiprazole, 0.22; placebo, 0.02). Changes in the Assessments of Involuntary Movement Scales were similar for the adjunctive aripiprazole and adjunctive placebo groups.

Autistic Disorder

In the short-term, placebo-controlled trials in autistic disorder in pediatric patients (6 to 17 years), the incidence of reported EPS-related events, excluding events related to akathisia, for aripiprazole-treated patients was 18% vs. 2% for placebo and the incidence of akathisia-related events for aripiprazole-treated patients was 3% vs. 9% for placebo.

In the pediatric (6 to 17 years) short-term autistic disorder trials, the Simpson Angus Rating Scale showed a significant difference between aripiprazole and placebo (aripiprazole, 0.1; placebo, −0.4). Changes in the Barnes Akathisia Scale and the Assessments of Involuntary Movement Scales were similar for the aripiprazole and placebo groups.

Agitation Associated with Schizophrenia or Bipolar Mania

In the placebo-controlled trials in patients with agitation associated with schizophrenia or bipolar mania, the incidence of reported EPS-related events excluding events related to akathisia for aripiprazole-treated patients was 2% vs. 2% for placebo and the incidence of akathisia-related events for aripiprazole-treated patients was 2% vs. 0% for placebo. Objectively collected data on the Simpson Angus Rating Scale (for EPS) and the Barnes Akathisia Scale (for akathisia) for all treatment groups did not show a difference between aripiprazole and placebo.

Dystonia

Symptoms of dystonia, prolonged abnormal contractions of muscle groups, may occur in susceptible individuals during the first few days of treatment. Dystonic symptoms include: spasm of the neck muscles, sometimes progressing to tightness of the throat, swallowing difficulty, difficulty breathing, and/or protrusion of the tongue. While these symptoms can occur at low doses, they occur more frequently and with greater severity with high potency and at higher doses of first generation antipsychotic drugs. An elevated risk of acute dystonia is observed in males and younger age groups. Class Effect:

Laboratory Test Abnormalities

A between group comparison for 3-week to 6-week, placebo-controlled trials in adults or 4-week to 8-week, placebo-controlled trials in pediatric patients (6 to 17 years) revealed no medically important differences between the aripiprazole and placebo groups in the proportions of patients experiencing potentially clinically significant changes in routine serum chemistry, hematology, or urinalysis parameters. Similarly, there were no aripiprazole/placebo differences in the incidence of discontinuations for changes in serum chemistry, hematology, or urinalysis in adult or pediatric patients.

ECG Changes

Between group comparisons for a pooled analysis of placebo-controlled trials in patients with schizophrenia, bipolar mania, or major depressive disorder revealed no significant differences between oral aripiprazole and placebo in the proportion of patients experiencing potentially important changes in ECG parameters. Aripiprazole was associated with a median increase in heart rate of 2 beats per minute compared to no increase among placebo patients.

In the pooled, placebo-controlled trials in patients with agitation associated with schizophrenia or bipolar mania, there were no significant differences between aripiprazole injection and placebo in the proportion of patients experiencing potentially important changes in ECG parameters, as measured by standard 12-lead ECGs.

Additional Findings Observed in Clinical Trials

Adverse Reactions in Long-Term, Double-Blind, Placebo-Controlled Trials

The adverse reactions reported in a 26-week, double-blind trial comparing oral ABILIFY and placebo in patients with schizophrenia were generally consistent with those reported in the short-term, placebo-controlled trials, except for a higher incidence of tremor [8% (12/153) for ABILIFY vs. 2% (3/153) for placebo]. In this study, the majority of the cases of tremor were of mild intensity (8/12 mild and 4/12 moderate), occurred early in therapy (9/12 ≤49 days), and were of limited duration (7/12 ≤10 days). Tremor infrequently led to discontinuation (<1%) of ABILIFY. In addition, in a long-term (52-week), active-controlled study, the incidence of tremor was 5% (40/859) for ABILIFY. A similar profile was observed in a long-term monotherapy study and a long-term adjunctive study with lithium and valproate in bipolar disorder.

Other Adverse Reactions Observed During the Premarketing Evaluation of Aripiprazole

Following is a list of MedDRA terms that reflect adverse reactions as defined in reported by patients treated with oral aripiprazole at multiple doses ≥2 mg/day during any phase of a trial within the database of 13,543 adult patients. All events assessed as possible adverse drug reactions have been included with the exception of more commonly occurring events. In addition, medically/clinically meaningful adverse reactions, particularly those that are likely to be useful to the prescriber or that have pharmacologic plausibility, have been included. Events already listed in other parts of or those considered in or have been excluded. Although the reactions reported occurred during treatment with aripiprazole, they were not necessarily caused by it. ADVERSE REACTIONS (6.1) ADVERSE REACTIONS , (6) WARNINGS AND PRECAUTIONS (5) OVERDOSAGE (10)

Events are further categorized by MedDRA system organ class and listed in order of decreasing frequency according to the following definitions: those occurring in at least 1/100 patients (only those not already listed in the tabulated results from placebo-controlled trials appear in this listing); those occurring in 1/100 to 1/1000 patients; and those occurring in fewer than 1/1000 patients.

Adults - Oral Administration

Blood and Lymphatic System Disorders:

- leukopenia, neutropenia, thrombocytopenia ≥1/1000 patients and <1/100 patients

Cardiac Disorders:

- bradycardia, palpitations, cardiopulmonary failure, myocardial infarction, cardio-respiratory arrest, atrioventricular block, extrasystoles, sinus tachycardia, atrial fibrillation, angina pectoris, myocardial ischemia; - atrial flutter, supraventricular tachycardia, ventricular tachycardia ≥1/1000 patients and <1/100 patients<1/1000 patients

Eye Disorders:

- photophobia, diplopia, eyelid edema, photopsia ≥1/1000 patients and <1/100 patients

Gastrointestinal Disorders:

- gastroesophageal reflux disease, swollen tongue, esophagitis; - pancreatitis ≥1/1000 patients and <1/100 patients<1/1000 patients

General Disorders and Administration Site Conditions:

- asthenia, peripheral edema, chest pain; - face edema, angioedema; - hypothermia ≥1/100 patients≥1/1000 patients and <1/100 patients<1/1000 patients

Hepatobiliary Disorders:

- hepatitis, jaundice <1/1000 patients

Immune System Disorders:

- hypersensitivity ≥1/1000 patients and <1/100 patients

Injury, Poisoning, and Procedural Complications:

- fall; - self mutilation; - heat stroke ≥1/100 patients≥1/1000 patients and <1/100 patients<1/1000 patients

Investigations:

- weight decreased, creatine phosphokinase increased; - hepatic enzyme increased, blood glucose increased, blood prolactin increased, blood urea increased, electrocardiogram QT prolonged, blood creatinine increased, blood bilirubin increased; - blood lactate dehydrogenase increased, glycosylated hemoglobin increased, gamma-glutamyl transferase increased ≥1/100 patients≥1/1000 patients and <1/100 patients<1/1000 patients

Metabolism and Nutrition Disorders:

- hyperlipidemia, anorexia, diabetes mellitus (including blood insulin increased, carbohydrate tolerance decreased, diabetes mellitus non-insulin-dependent, glucose tolerance impaired, glycosuria, glucose urine, glucose urine present), hyperglycemia, hypokalemia, hyponatremia, hypoglycemia, polydipsia; - diabetic ketoacidosis ≥1/1000 patients and <1/100 patients<1/1000 patients

Musculoskeletal and Connective Tissue Disorders:

- muscle rigidity, muscular weakness, muscle tightness, mobility decreased; - rhabdomyolysis ≥1/1000 patients and <1/100 patients<1/1000 patients

Nervous System Disorders:

- coordination abnormal; - speech disorder, parkinsonism, memory impairment, cogwheel rigidity, cerebrovascular accident, hypokinesia, tardive dyskinesia, hypotonia, myoclonus, hypertonia, akinesia, bradykinesia; - Grand Mal convulsion, choreoathetosis ≥1/100 patients≥1/1000 patients and <1/100 patients<1/1000 patients

Psychiatric Disorders:

- suicidal ideation; - aggression, loss of libido, suicide attempt, hostility, libido increased, anger, anorgasmia, delirium, intentional self injury, completed suicide, tic, homicidal ideation; - catatonia, sleep walking ≥1/100 patients≥1/1000 patients and <1/100 patients<1/1000 patients

Renal and Urinary Disorders:

- urinary retention, polyuria, nocturia ≥1/1000 patients and <1/100 patients

Reproductive System and Breast Disorders:

- menstruation irregular, erectile dysfunction, amenorrhea, breast pain; - gynaecomastia, priapism ≥1/1000 patients and <1/100 patients<1/1000 patients

Respiratory, Thoracic, and Mediastinal Disorders:

- nasal congestion, dyspnea, pneumonia aspiration ≥1/100 patients

Skin and Subcutaneous Tissue Disorders:

- rash (including erythematous, exfoliative, generalized, macular, maculopapular, papular rash; acneiform, allergic, contact, exfoliative, seborrheic dermatitis, neurodermatitis, and drug eruption), hyperhydrosis; - pruritus, photosensitivity reaction, alopecia, urticaria ≥1/100 patients≥1/1000 patients and <1/100 patients

Vascular Disorders:

- hypertension; - hypotension ≥1/100 patients≥1/1000 patients and <1/100 patients

Pediatric Patients - Oral Administration

Most adverse events observed in the pooled database of 920 pediatric patients, aged 6 to 17 years, were also observed in the adult population. Additional adverse reactions observed in the pediatric population are listed below.

Gastrointestinal Disorders:

- tongue dry, tongue spasm ≥1/1000 patients and <1/100 patients

Investigations:

- blood insulin increased ≥1/100 patients

Nervous System Disorders:

- sleep talking ≥1/1000 patients and <1/100 patients

Skin and Subcutaneous Tissue Disorders:

- hirsutism ≥1/1000 patients and <1/100 patients

Adults - Intramuscular Injection

Most adverse reactions observed in the pooled database of 749 adult patients treated with aripiprazole injection, were also observed in the adult population treated with oral aripiprazole. Additional adverse reactions observed in the aripiprazole injection population are listed below.

General Disorders and Administration Site Conditions:

- injection site reaction; - venipuncture site bruise ≥1/100 patients≥1/1000 patients and <1/100 patients

6.3 Postmarketing Experience

The following adverse reactions have been identified during postapproval use of ABILIFY. Because these reactions are reported voluntarily from a population of uncertain size, it is not always possible to establish a causal relationship to drug exposure: rare occurrences of allergic reaction (anaphylactic reaction, angioedema, laryngospasm, pruritus/urticaria, or oropharyngeal spasm), and blood glucose fluctuation.

7 DRUG INTERACTIONS

Given the primary CNS effects of aripiprazole, caution should be used when ABILIFY is taken in combination with other centrally-acting drugs or alcohol.

Due to its alpha adrenergic antagonism, aripiprazole has the potential to enhance the effect of certain antihypertensive agents.

7.1 Potential for Other Drugs to Affect ABILIFY

Aripiprazole is not a substrate of CYP1A1, CYP1A2, CYP2A6, CYP2B6, CYP2C8, CYP2C9, CYP2C19, or CYP2E1 enzymes. Aripiprazole also does not undergo direct glucuronidation. This suggests that an interaction of aripiprazole with inhibitors or inducers of these enzymes, or other factors, like smoking, is unlikely.

Both CYP3A4 and CYP2D6 are responsible for aripiprazole metabolism. Agents that induce CYP3A4 (eg, carbamazepine) could cause an increase in aripiprazole clearance and lower blood levels. Inhibitors of CYP3A4 (eg, ketoconazole) or CYP2D6 (eg, quinidine, fluoxetine, or paroxetine) can inhibit aripiprazole elimination and cause increased blood levels.

Ketoconazole and Other CYP3A4 Inhibitors

Coadministration of ketoconazole (200 mg/day for 14 days) with a 15 mg single dose of aripiprazole increased the AUC of aripiprazole and its active metabolite by 63% and 77%, respectively. The effect of a higher ketoconazole dose (400 mg/day) has not been studied. When ketoconazole is given concomitantly with aripiprazole, the aripiprazole dose should be reduced to one-half of its normal dose. Other strong inhibitors of CYP3A4 (itraconazole) would be expected to have similar effects and need similar dose reductions; moderate inhibitors (erythromycin, grapefruit juice) have not been studied. When the CYP3A4 inhibitor is withdrawn from the combination therapy, the aripiprazole dose should be increased.

Quinidine and Other CYP2D6 Inhibitors

Coadministration of a 10 mg single dose of aripiprazole with quinidine (166 mg/day for 13 days), a potent inhibitor of CYP2D6, increased the AUC of aripiprazole by 112% but decreased the AUC of its active metabolite, dehydro-aripiprazole, by 35%. Aripiprazole dose should be reduced to one-half of its normal dose when quinidine is given concomitantly with aripiprazole. Other significant inhibitors of CYP2D6, such as fluoxetine or paroxetine, would be expected to have similar effects and should lead to similar dose reductions. When the CYP2D6 inhibitor is withdrawn from the combination therapy, the aripiprazole dose should be increased. When adjunctive ABILIFY is administered to patients with major depressive disorder, ABILIFY should be administered without dosage adjustment as specified in . DOSAGE AND ADMINISTRATION (2.3)

Carbamazepine and Other CYP3A4 Inducers

Coadministration of carbamazepine (200 mg twice daily), a potent CYP3A4 inducer, with aripiprazole (30 mg/day) resulted in an approximate 70% decrease in Cmax and AUC values of both aripiprazole and its active metabolite, dehydro-aripiprazole. When carbamazepine is added to aripiprazole therapy, aripiprazole dose should be doubled. Additional dose increases should be based on clinical evaluation. When carbamazepine is withdrawn from the combination therapy, the aripiprazole dose should be reduced.

7.2 Potential for ABILIFY to Affect Other Drugs

Aripiprazole is unlikely to cause clinically important pharmacokinetic interactions with drugs metabolized by cytochrome P450 enzymes. In studies, 10 mg/day to 30 mg/day doses of aripiprazole had no significant effect on metabolism by CYP2D6 (dextromethorphan), CYP2C9 (warfarin), CYP2C19 (omeprazole, warfarin), and CYP3A4 (dextromethorphan) substrates. Additionally, aripiprazole and dehydro-aripiprazole did not show potential for altering CYP1A2-mediated metabolism . in vivoin vitro

No effect of aripiprazole was seen on the pharmacokinetics of lithium or valproate.

Alcohol

There was no significant difference between aripiprazole coadministered with ethanol and placebo coadministered with ethanol on performance of gross motor skills or stimulus response in healthy subjects. As with most psychoactive medications, patients should be advised to avoid alcohol while taking ABILIFY.

7.3 Drugs Having No Clinically Important Interactions with ABILIFY

Famotidine

Coadministration of aripiprazole (given in a single dose of 15 mg) with a 40 mg single dose of the H antagonist famotidine, a potent gastric acid blocker, decreased the solubility of aripiprazole and, hence, its rate of absorption, reducing by 37% and 21% the Cmax of aripiprazole and dehydro-aripiprazole, respectively, and by 13% and 15%, respectively, the extent of absorption (AUC). No dosage adjustment of aripiprazole is required when administered concomitantly with famotidine.2

Valproate

When valproate (500 mg/day-1500 mg/day) and aripiprazole (30 mg/day) were coadministered, at steady-state the Cmax and AUC of aripiprazole were decreased by 25%. No dosage adjustment of aripiprazole is required when administered concomitantly with valproate.

When aripiprazole (30 mg/day) and valproate (1000 mg/day) were coadministered, at steady-state there were no clinically significant changes in the Cmax or AUC of valproate. No dosage adjustment of valproate is required when administered concomitantly with aripiprazole.

Lithium

A pharmacokinetic interaction of aripiprazole with lithium is unlikely because lithium is not bound to plasma proteins, is not metabolized, and is almost entirely excreted unchanged in urine. Coadministration of therapeutic doses of lithium (1200 mg/day-1800 mg/day) for 21 days with aripiprazole (30 mg/day) did not result in clinically significant changes in the pharmacokinetics of aripiprazole or its active metabolite, dehydro-aripiprazole (Cmax and AUC increased by less than 20%). No dosage adjustment of aripiprazole is required when administered concomitantly with lithium.

Coadministration of aripiprazole (30 mg/day) with lithium (900 mg/day) did not result in clinically significant changes in the pharmacokinetics of lithium. No dosage adjustment of lithium is required when administered concomitantly with aripiprazole.

Lamotrigine

Coadministration of 10 mg/day to 30 mg/day oral doses of aripiprazole for 14 days to patients with bipolar I disorder had no effect on the steady-state pharmacokinetics of 100 mg/day to 400 mg/day lamotrigine, a UDP-glucuronosyltransferase 1A4 substrate. No dosage adjustment of lamotrigine is required when aripiprazole is added to lamotrigine.

Dextromethorphan

Aripiprazole at doses of 10 mg/day to 30 mg/day for 14 days had no effect on dextromethorphan's O-dealkylation to its major metabolite, dextrorphan, a pathway dependent on CYP2D6 activity. Aripiprazole also had no effect on dextromethorphan's N-demethylation to its metabolite 3-methoxymorphinan, a pathway dependent on CYP3A4 activity. No dosage adjustment of dextromethorphan is required when administered concomitantly with aripiprazole.

Warfarin

Aripiprazole 10 mg/day for 14 days had no effect on the pharmacokinetics of R-warfarin and S-warfarin or on the pharmacodynamic end point of International Normalized Ratio, indicating the lack of a clinically relevant effect of aripiprazole on CYP2C9 and CYP2C19 metabolism or the binding of highly protein-bound warfarin. No dosage adjustment of warfarin is required when administered concomitantly with aripiprazole.

Omeprazole

Aripiprazole 10 mg/day for 15 days had no effect on the pharmacokinetics of a single 20 mg dose of omeprazole, a CYP2C19 substrate, in healthy subjects. No dosage adjustment of omeprazole is required when administered concomitantly with aripiprazole.

Lorazepam

Coadministration of lorazepam injection (2 mg) and aripiprazole injection (15 mg) to healthy subjects (n=40: 35 males and 5 females; ages 19-45 years old) did not result in clinically important changes in the pharmacokinetics of either drug. No dosage adjustment of aripiprazole is required when administered concomitantly with lorazepam. However, the intensity of sedation was greater with the combination as compared to that observed with aripiprazole alone and the orthostatic hypotension observed was greater with the combination as compared to that observed with lorazepam alone . [see WARNINGS AND PRECAUTIONS ] (5.6)

Escitalopram

Coadministration of 10 mg/day oral doses of aripiprazole for 14 days to healthy subjects had no effect on the steady-state pharmacokinetics of 10 mg/day escitalopram, a substrate of CYP2C19 and CYP3A4. No dosage adjustment of escitalopram is required when aripiprazole is added to escitalopram.

Venlafaxine

Coadministration of 10 mg/day to 20 mg/day oral doses of aripiprazole for 14 days to healthy subjects had no effect on the steady-state pharmacokinetics of venlafaxine and O-desmethylvenlafaxine following 75 mg/day venlafaxine XR, a CYP2D6 substrate. No dosage adjustment of venlafaxine is required when aripiprazole is added to venlafaxine.

Fluoxetine, Paroxetine, and Sertraline

A population pharmacokinetic analysis in patients with major depressive disorder showed no substantial change in plasma concentrations of fluoxetine (20 mg/day or 40 mg/day), paroxetine CR (37.5 mg/day or 50 mg/day), or sertraline (100 mg/day or 150 mg/day) dosed to steady-state. The steady-state plasma concentrations of fluoxetine and norfluoxetine increased by about 18% and 36%, respectively, and concentrations of paroxetine decreased by about 27%. The steady-state plasma concentrations of sertraline and desmethylsertraline were not substantially changed when these antidepressant therapies were coadministered with aripiprazole. Aripiprazole dosing was 2 mg/day to 15 mg/day (when given with fluoxetine or paroxetine) or 2 mg/day to 20 mg/day (when given with sertraline).

8 USE IN SPECIFIC POPULATIONS

In general, no dosage adjustment for ABILIFY is required on the basis of a patient’s age, gender, race, smoking status, hepatic function, or renal function . [see DOSAGE AND ADMINISTRATION ] (2.5)

8.1 Pregnancy

Teratogenic Effects

In animal studies, aripiprazole demonstrated developmental toxicity, including possible teratogenic effects in rats and rabbits. Pregnancy Category C:

Pregnant rats were treated with oral doses of 3 mg/kg/day, 10 mg/kg/day, and 30 mg/kg/day (1 times, 3 times, and 10 times the maximum recommended human dose [MRHD] on a mg/m basis) of aripiprazole during the period of organogenesis. Gestation was slightly prolonged at 30 mg/kg. Treatment caused a slight delay in fetal development, as evidenced by decreased fetal weight (30 mg/kg), undescended testes (30 mg/kg), and delayed skeletal ossification (10 mg/kg and 30 mg/kg). There were no adverse effects on embryofetal or pup survival. Delivered offspring had decreased body weights (10 mg/kg and 30 mg/kg), and increased incidences of hepatodiaphragmatic nodules and diaphragmatic hernia at 30 mg/kg (the other dose groups were not examined for these findings). A low incidence of diaphragmatic hernia was also seen in the fetuses exposed to 30 mg/kg. Postnatally, delayed vaginal opening was seen at 10 mg/kg and 30 mg/kg and impaired reproductive performance (decreased fertility rate, corpora lutea, implants, live fetuses, and increased post-implantation loss, likely mediated through effects on female offspring) was seen at 30 mg/kg. Some maternal toxicity was seen at 30 mg/kg; however, there was no evidence to suggest that these developmental effects were secondary to maternal toxicity.^2

In pregnant rats receiving aripiprazole injection intravenously (3 mg/kg/day, 9 mg/kg/day, and 27 mg/kg/day) during the period of organogenesis, decreased fetal weight and delayed skeletal ossification were seen at the highest dose, which also caused some maternal toxicity.

Pregnant rabbits were treated with oral doses of 10 mg/kg/day, 30 mg/kg/day, and 100 mg/kg/day (2 times, 3 times, and 11 times human exposure at MRHD based on AUC and 6 times, 19 times, and 65 times the MRHD based on mg/m) of aripiprazole during the period of organogenesis. Decreased maternal food consumption and increased abortions were seen at 100 mg/kg. Treatment caused increased fetal mortality (100 mg/kg), decreased fetal weight (30 mg/kg and 100 mg/kg), increased incidence of a skeletal abnormality (fused sternebrae at 30 mg/kg and 100 mg/kg), and minor skeletal variations (100 mg/kg).^2

In pregnant rabbits receiving aripiprazole injection intravenously (3 mg/kg/day, 10 mg/kg/day, and 30 mg/kg/day) during the period of organogenesis, the highest dose, which caused pronounced maternal toxicity, resulted in decreased fetal weight, increased fetal abnormalities (primarily skeletal), and decreased fetal skeletal ossification. The fetal no-effect dose was 10 mg/kg, which produced 5 times the human exposure at the MRHD based on AUC and is 6 times the MRHD based on mg/m .^2

In a study in which rats were treated with oral doses of 3 mg/kg/day, 10 mg/kg/day, and 30 mg/kg/day (1 times, 3 times, and 10 times the MRHD on a mg/m basis) of aripiprazole perinatally and postnatally (from day 17 of gestation through day 21 postpartum), slight maternal toxicity and slightly prolonged gestation were seen at 30 mg/kg. An increase in stillbirths and decreases in pup weight (persisting into adulthood) and survival were seen at this dose.^2

In rats receiving aripiprazole injection intravenously (3 mg/kg/day, 8 mg/kg/day, and 20 mg/kg/day) from day 6 of gestation through day 20 postpartum, an increase in stillbirths was seen at 8 mg/kg and 20 mg/kg, and decreases in early postnatal pup weights and survival were seen at 20 mg/kg. These doses produced some maternal toxicity. There were no effects on postnatal behavioral and reproductive development.

Non-teratogenic Effects

There are no adequate and well-controlled studies in pregnant women. It is not known whether aripiprazole can cause fetal harm when administered to a pregnant woman or can affect reproductive capacity. Neonates exposed to antipsychotic drugs during the third trimester of pregnancy are at risk for extrapyramidal and/or withdrawal symptoms following delivery. There have been reports of agitation, hypertonia, hypotonia, tremor, somnolence, respiratory distress and feeding disorder in these neonates. These complications have varied in severity; while in some cases symptoms have been self-limited, in other cases neonates have required intensive care unit support and prolonged hospitalization.

Aripiprazole should be used during pregnancy only if the potential benefit justifies the potential risk to the fetus.

8.2 Labor and Delivery

The effect of aripiprazole on labor and delivery in humans is unknown.

8.3 Nursing Mothers

Aripiprazole is excreted in human breast milk. A decision should be made whether to discontinue nursing or to discontinue the drug, taking into account the importance of the drug to the mother.

8.4 Pediatric Use

Safety and effectiveness in pediatric patients with major depressive disorder or agitation associated with schizophrenia or bipolar mania have not been established.

Safety and effectiveness in pediatric patients with schizophrenia were established in a 6-week, placebo-controlled clinical trial in 202 pediatric patients aged 13 to 17 years . Although maintenance efficacy in pediatric patients has not been systematically evaluated, maintenance efficacy can be extrapolated from adult data along with comparisons of aripiprazole pharmacokinetic parameters in adult and pediatric patients. [see INDICATIONS AND USAGE , DOSAGE AND ADMINISTRATION , ADVERSE REACTIONS , and CLINICAL STUDIES ] (1.1) (2.1) (6.2) (14.1)

Safety and effectiveness in pediatric patients with bipolar mania were established in a 4-week, placebo-controlled clinical trial in 197 pediatric patients aged 10 to 17 years . Although maintenance efficacy in pediatric patients has not been systematically evaluated, maintenance efficacy can be extrapolated from adult data along with comparisons of aripiprazole pharmacokinetic parameters in adult and pediatric patients. [see INDICATIONS AND USAGE , DOSAGE AND ADMINISTRATION , ADVERSE REACTIONS , and CLINICAL STUDIES ] (1.2) (2.2) (6.2) (14.2)

The efficacy of adjunctive ABILIFY with concomitant lithium or valproate in the treatment of manic or mixed episodes in pediatric patients has not been systematically evaluated. However, such efficacy and lack of pharmacokinetic interaction between aripiprazole and lithium or valproate can be extrapolated from adult data, along with comparisons of aripiprazole pharmacokinetic parameters in adult and pediatric patients.

Safety and effectiveness in pediatric patients demonstrating irritability associated with autistic disorder were established in two 8-week, placebo-controlled clinical trials in 212 pediatric patients aged 6 to 17 years , , . A maintenance trial was conducted in pediatric patients (6 to 17 years of age) with irritability associated with autistic disorder. The first phase of this trial was an open-label, flexibly dosed (aripiprazole 2 to 15 mg/day) phase in which patients were stabilized (defined as > 25% improvement on the ABC-I subscale, and a CGI-I rating of “much improved” or “very much improved”) on ABILIFY for 12 consecutive weeks. Overall, 85 patients were stabilized and entered the second, 16-week, double-blind phase where they were randomized to either continue ABILIFY treatment or switch to placebo. In this trial, the efficacy of ABILIFY for the maintenance treatment of irritability associated with autistic disorder was not established. [see INDICATIONS AND USAGE (1.4) DOSAGE AND ADMINISTRATION (2.4) ADVERSE REACTIONS , and CLINICAL STUDIES ] (6.2) (14.4)

The pharmacokinetics of aripiprazole and dehydro-aripiprazole in pediatric patients, 10 to 17 years of age, were similar to those in adults after correcting for the differences in body weight.

8.5 Geriatric Use

In formal single-dose pharmacokinetic studies (with aripiprazole given in a single dose of 15 mg), aripiprazole clearance was 20% lower in elderly (≥65 years) subjects compared to younger adult subjects (18 to 64 years). There was no detectable age effect, however, in the population pharmacokinetic analysis in schizophrenia patients. Also, the pharmacokinetics of aripiprazole after multiple doses in elderly patients appeared similar to that observed in young, healthy subjects. No dosage adjustment is recommended for elderly patients . [see also and WARNINGS AND PRECAUTIONS ] BOXED WARNING (5.1)

Of the 13,543 patients treated with oral aripiprazole in clinical trials, 1073 (8%) were ≥65 years old and 799 (6%) were ≥75 years old. The majority (81%) of the 1073 patients were diagnosed with Dementia of the Alzheimer's type.

Placebo-controlled studies of oral aripiprazole in schizophrenia, bipolar mania, or major depressive disorder did not include sufficient numbers of subjects aged 65 and over to determine whether they respond differently from younger subjects.

Of the 749 patients treated with aripiprazole injection in clinical trials, 99 (13%) were ≥65 years old and 78 (10%) were ≥75 years old. Placebo-controlled studies of aripiprazole injection in patients with agitation associated with schizophrenia or bipolar mania did not include sufficient numbers of subjects aged 65 and over to determine whether they respond differently from younger subjects.

Studies of elderly patients with psychosis associated with Alzheimer's disease have suggested that there may be a different tolerability profile in this population compared to younger patients with schizophrenia . The safety and efficacy of ABILIFY in the treatment of patients with psychosis associated with Alzheimer's disease has not been established. If the prescriber elects to treat such patients with ABILIFY, vigilance should be exercised. [see also and WARNINGS AND PRECAUTIONS ] BOXED WARNING (5.1)

8.6 Renal Impairment

In patients with severe renal impairment (creatinine clearance <30 mL/min), Cmax of aripiprazole (given in a single dose of 15 mg) and dehydro-aripiprazole increased by 36% and 53%, respectively, but AUC was 15% lower for aripiprazole and 7% higher for dehydro-aripiprazole. Renal excretion of both unchanged aripiprazole and dehydro-aripiprazole is less than 1% of the dose. No dosage adjustment is required in subjects with renal impairment.

8.7 Hepatic Impairment

In a single-dose study (15 mg of aripiprazole) in subjects with varying degrees of liver cirrhosis (Child-Pugh Classes A, B, and C), the AUC of aripiprazole, compared to healthy subjects, increased 31% in mild HI, increased 8% in moderate HI, and decreased 20% in severe HI. None of these differences would require dose adjustment.

8.8 Gender

Cmax and AUC of aripiprazole and its active metabolite, dehydro-aripiprazole, are 30% to 40% higher in women than in men, and correspondingly, the apparent oral clearance of aripiprazole is lower in women. These differences, however, are largely explained by differences in body weight (25%) between men and women. No dosage adjustment is recommended based on gender.

8.9 Race

Although no specific pharmacokinetic study was conducted to investigate the effects of race on the disposition of aripiprazole, population pharmacokinetic evaluation revealed no evidence of clinically significant race-related differences in the pharmacokinetics of aripiprazole. No dosage adjustment is recommended based on race.

8.10 Smoking

Based on studies utilizing human liver enzymes , aripiprazole is not a substrate for CYP1A2 and also does not undergo direct glucuronidation. Smoking should, therefore, not have an effect on the pharmacokinetics of aripiprazole. Consistent with these results, population pharmacokinetic evaluation did not reveal any significant pharmacokinetic differences between smokers and nonsmokers. No dosage adjustment is recommended based on smoking status. in vitroin vitro

9 DRUG ABUSE AND DEPENDENCE

9.1 Controlled Substance

ABILIFY is not a controlled substance.

9.2 Abuse and Dependence

Aripiprazole has not been systematically studied in humans for its potential for abuse, tolerance, or physical dependence. In physical dependence studies in monkeys, withdrawal symptoms were observed upon abrupt cessation of dosing. While the clinical trials did not reveal any tendency for any drug-seeking behavior, these observations were not systematic and it is not possible to predict on the basis of this limited experience the extent to which a CNS-active drug will be misused, diverted, and/or abused once marketed. Consequently, patients should be evaluated carefully for a history of drug abuse, and such patients should be observed closely for signs of ABILIFY misuse or abuse (eg, development of tolerance, increases in dose, drug-seeking behavior).

10 OVERDOSAGE

MedDRA terminology has been used to classify the adverse reactions.

10.1 Human Experience

In clinical trials and in postmarketing experience, adverse reactions of deliberate or accidental overdosage with oral aripiprazole have been reported worldwide. These include overdoses with oral aripiprazole alone and in combination with other substances. No fatality was reported with aripiprazole alone. The largest known dose with a known outcome involved acute ingestion of 1260 mg of oral aripiprazole (42 times the maximum recommended daily dose) by a patient who fully recovered. Deliberate or accidental overdosage was also reported in children (age 12 and younger) involving oral aripiprazole ingestions up to 195 mg with no fatalities.

Common adverse reactions (reported in at least 5% of all overdose cases) reported with oral aripiprazole overdosage (alone or in combination with other substances) include vomiting, somnolence, and tremor. Other clinically important signs and symptoms observed in one or more patients with aripiprazole overdoses (alone or with other substances) include acidosis, aggression, aspartate aminotransferase increased, atrial fibrillation, bradycardia, coma, confusional state, convulsion, blood creatine phosphokinase increased, depressed level of consciousness, hypertension, hypokalemia, hypotension, lethargy, loss of consciousness, QRS complex prolonged, QT prolonged, pneumonia aspiration, respiratory arrest, status epilepticus, and tachycardia.

10.2 Management of Overdosage

No specific information is available on the treatment of overdose with aripiprazole. An electrocardiogram should be obtained in case of overdosage and if QT interval prolongation is present, cardiac monitoring should be instituted. Otherwise, management of overdose should concentrate on supportive therapy, maintaining an adequate airway, oxygenation and ventilation, and management of symptoms. Close medical supervision and monitoring should continue until the patient recovers.

In the event of an overdose of ABILIFY, an early charcoal administration may be useful in partially preventing the absorption of aripiprazole. Administration of 50 g of activated charcoal, one hour after a single 15 mg oral dose of aripiprazole, decreased the mean AUC and Cmax of aripiprazole by 50%. Charcoal:

Although there is no information on the effect of hemodialysis in treating an overdose with aripiprazole, hemodialysis is unlikely to be useful in overdose management since aripiprazole is highly bound to plasma proteins. Hemodialysis:

11 DESCRIPTION

Aripiprazole is a psychotropic drug that is available as ABILIFY (aripiprazole) Tablets, ABILIFY DISCMELT (aripiprazole) Orally Disintegrating Tablets, ABILIFY (aripiprazole) Oral Solution, and ABILIFY (aripiprazole) Injection, a solution for intramuscular injection. Aripiprazole is 7-[4-[4-(2,3-dichlorophenyl)-1-piperazinyl]butoxy]-3,4-dihydrocarbostyril. The empirical formula is C H Cl N O and its molecular weight is 448.38. The chemical structure is:®®®®2327232

ABILIFY Tablets are available in 2 mg, 5 mg, 10 mg, 15 mg, 20 mg, and 30 mg strengths. Inactive ingredients include cornstarch, hydroxypropyl cellulose, lactose monohydrate, magnesium stearate, and microcrystalline cellulose. Colorants include ferric oxide (yellow or red) and FD&C Blue No. 2 Aluminum Lake.

ABILIFY DISCMELT Orally Disintegrating Tablets are available in 10 mg and 15 mg strengths. Inactive ingredients include acesulfame potassium, aspartame, calcium silicate, croscarmellose sodium, crospovidone, crème de vanilla (natural and artificial flavors), magnesium stearate, microcrystalline cellulose, silicon dioxide, tartaric acid, and xylitol. Colorants include ferric oxide (yellow or red) and FD&C Blue No. 2 Aluminum Lake.

ABILIFY Oral Solution is a clear, colorless to light-yellow solution available in a concentration of 1 mg/mL. The inactive ingredients for this solution include disodium edetate, fructose, glycerin, dl-lactic acid, methylparaben, propylene glycol, propylparaben, sodium hydroxide, sucrose, and purified water. The oral solution is flavored with natural orange cream and other natural flavors.

ABILIFY Injection is available in single-dose vials as a ready-to-use, 9.75 mg/1.3 mL (7.5 mg/mL) clear, colorless, sterile, aqueous solution for intramuscular use only. Inactive ingredients for this solution include 150 mg/mL of sulfobutylether β-cyclodextrin (SBECD), tartaric acid, sodium hydroxide, and water for injection.

12 CLINICAL PHARMACOLOGY

12.1 Mechanism of Action

The mechanism of action of aripiprazole, as with other drugs having efficacy in schizophrenia, bipolar disorder, major depressive disorder, irritability associated with autistic disorder, and agitation associated with schizophrenia or bipolar disorder, is unknown. However, it has been proposed that the efficacy of aripiprazole is mediated through a combination of partial agonist activity at D and 5-HT receptors and antagonist activity at 5-HT receptors. Actions at receptors other than D , 5-HT , and 5-HT may explain some of the other clinical effects of aripiprazole (eg, the orthostatic hypotension observed with aripiprazole may be explained by its antagonist activity at adrenergic alpha receptors).21A2A21A2A1

12.2 Pharmacodynamics

Aripiprazole exhibits high affinity for dopamine D and D , serotonin 5-HT and 5-HT receptors (K values of 0.34 nM, 0.8 nM, 1.7 nM, and 3.4 nM, respectively), moderate affinity for dopamine D , serotonin 5-HT and 5-HT , alpha -adrenergic and histamine H receptors (K values of 44 nM, 15 nM, 39 nM, 57 nM, and 61 nM, respectively), and moderate affinity for the serotonin reuptake site (K =98 nM). Aripiprazole has no appreciable affinity for cholinergic muscarinic receptors (IC >1000 nM). Aripiprazole functions as a partial agonist at the dopamine D and the serotonin 5-HT receptors, and as an antagonist at serotonin 5-HT receptor.231A2Ai42C711ii5021A2A

12.3 Pharmacokinetics

ABILIFY activity is presumably primarily due to the parent drug, aripiprazole, and to a lesser extent, to its major metabolite, dehydro-aripiprazole, which has been shown to have affinities for D receptors similar to the parent drug and represents 40% of the parent drug exposure in plasma. The mean elimination half-lives are about 75 hours and 94 hours for aripiprazole and dehydro-aripiprazole, respectively. Steady-state concentrations are attained within 14 days of dosing for both active moieties. Aripiprazole accumulation is predictable from single-dose pharmacokinetics. At steady-state, the pharmacokinetics of aripiprazole are dose-proportional. Elimination of aripiprazole is mainly through hepatic metabolism involving two P450 isozymes, CYP2D6 and CYP3A4.2

Pharmacokinetic studies showed that ABILIFY DISCMELT Orally Disintegrating Tablets are bioequivalent to ABILIFY Tablets.

ORAL ADMINISTRATION

Absorption

Aripiprazole is well absorbed after administration of the tablet, with peak plasma concentrations occurring within 3 hours to 5 hours; the absolute oral bioavailability of the tablet formulation is 87%. ABILIFY can be administered with or without food. Administration of a 15 mg ABILIFY Tablet with a standard high-fat meal did not significantly affect the Cmax or AUC of aripiprazole or its active metabolite, dehydro-aripiprazole, but delayed Tmax by 3 hours for aripiprazole and 12 hours for dehydro-aripiprazole. Tablet:

Aripiprazole is well absorbed when administered orally as the solution. At equivalent doses, the plasma concentrations of aripiprazole from the solution were higher than that from the tablet formulation. In a relative bioavailability study comparing the pharmacokinetics of 30 mg aripiprazole as the oral solution to 30 mg aripiprazole tablets in healthy subjects, the solution to tablet ratios of geometric mean Cmax and AUC values were 122% and 114%, respectively . The single-dose pharmacokinetics of aripiprazole were linear and dose-proportional between the doses of 5 mg to 30 mg. Oral Solution:[see DOSAGE AND ADMINISTRATION ] (2.6)

Distribution

The steady-state volume of distribution of aripiprazole following intravenous administration is high (404 L or 4.9 L/kg), indicating extensive extravascular distribution. At therapeutic concentrations, aripiprazole and its major metabolite are greater than 99% bound to serum proteins, primarily to albumin. In healthy human volunteers administered 0.5 mg/day to 30 mg/day aripiprazole for 14 days, there was dose-dependent D receptor occupancy indicating brain penetration of aripiprazole in humans.2

Metabolism and Elimination

Aripiprazole is metabolized primarily by three biotransformation pathways: dehydrogenation, hydroxylation, and N-dealkylation. Based on studies, CYP3A4 and CYP2D6 enzymes are responsible for dehydrogenation and hydroxylation of aripiprazole, and N-dealkylation is catalyzed by CYP3A4. Aripiprazole is the predominant drug moiety in the systemic circulation. At steady-state, dehydro-aripiprazole, the active metabolite, represents about 40% of aripiprazole AUC in plasma. in vitro

Approximately 8% of Caucasians and 3–8% of Black/African Americans lack the capacity to metabolize CYP2D6 substrates and are classified as poor metabolizers (PM), whereas the rest are extensive metabolizers (EM). PMs have about an 80% increase in aripiprazole exposure and about a 30% decrease in exposure to the active metabolite compared to EMs, resulting in about a 60% higher exposure to the total active moieties from a given dose of aripiprazole compared to EMs. Coadministration of ABILIFY with known inhibitors of CYP2D6, such as quinidine or fluoxetine in EMs, approximately doubles aripiprazole plasma exposure, and dose adjustment is needed . Similarly, PMs have higher exposure to aripiprazole compared to EMs; hence, PMs should have their initial dose reduced by one-half. Laboratory tests are available to identify CYP2D6 PMs. The mean elimination half-lives are about 75 hours and 146 hours for aripiprazole in EMs and PMs, respectively. Aripiprazole does not inhibit or induce the CYP2D6 pathway. [see DRUG INTERACTIONS ] (7.1)

Following a single oral dose of [ C]-labeled aripiprazole, approximately 25% and 55% of the administered radioactivity was recovered in the urine and feces, respectively. Less than 1% of unchanged aripiprazole was excreted in the urine and approximately 18% of the oral dose was recovered unchanged in the feces.^14

INTRAMUSCULAR ADMINISTRATION

In two pharmacokinetic studies of aripiprazole injection administered intramuscularly to healthy subjects, the median times to the peak plasma concentrations were at 1 hour and 3 hours. A 5 mg intramuscular injection of aripiprazole had an absolute bioavailability of 100%. The geometric mean maximum concentration achieved after an intramuscular dose was on average 19% higher than the Cmax of the oral tablet. While the systemic exposure over 24 hours was generally similar between aripiprazole injection given intramuscularly and after oral tablet administration, the aripiprazole AUC in the first 2 hours after an intramuscular injection was 90% greater than the AUC after the same dose as a tablet. In stable patients with schizophrenia or schizoaffective disorder, the pharmacokinetics of aripiprazole after intramuscular administration were linear over a dose range of 1 mg to 45 mg. Although the metabolism of aripiprazole injection was not systematically evaluated, the intramuscular route of administration would not be expected to alter the metabolic pathways.

13 NONCLINICAL TOXICOLOGY

13.1 Carcinogenesis, Mutagenesis, Impairment of Fertility

Carcinogenesis

Lifetime carcinogenicity studies were conducted in ICR mice and in Sprague-Dawley (SD) and F344 rats. Aripiprazole was administered for 2 years in the diet at doses of 1 mg/kg/day, 3 mg/kg/day, 10 mg/kg/day, and 30 mg/kg/day to ICR mice and 1 mg/kg/day, 3 mg/kg/day, and 10 mg/kg/day to F344 rats (0.2 times to 5 times and 0.3 times to 3 times the maximum recommended human dose [MRHD] based on mg/m , respectively). In addition, SD rats were dosed orally for 2 years at 10 mg/kg/day, 20 mg/kg/day, 40 mg/kg/day, and 60 mg/kg/day (3 times to 19 times the MRHD based on mg/m). Aripiprazole did not induce tumors in male mice or rats. In female mice, the incidences of pituitary gland adenomas and mammary gland adenocarcinomas and adenoacanthomas were increased at dietary doses of 3 mg/kg/day to 30 mg/kg/day (0.1 times to 0.9 times human exposure at MRHD based on AUC and 0.5 times to 5 times the MRHD based on mg/m). In female rats, the incidence of mammary gland fibroadenomas was increased at a dietary dose of 10 mg/kg/day (0.1 times human exposure at MRHD based on AUC and 3 times the MRHD based on mg/m); and the incidences of adrenocortical carcinomas and combined adrenocortical adenomas/carcinomas were increased at an oral dose of 60 mg/kg/day (14 times human exposure at MRHD based on AUC and 19 times the MRHD based on mg/m).^2^2^2^2^2

Proliferative changes in the pituitary and mammary gland of rodents have been observed following chronic administration of other antipsychotic agents and are considered prolactin-mediated. Serum prolactin was not measured in the aripiprazole carcinogenicity studies. However, increases in serum prolactin levels were observed in female mice in a 13-week dietary study at the doses associated with mammary gland and pituitary tumors. Serum prolactin was not increased in female rats in 4-week and 13-week dietary studies at the dose associated with mammary gland tumors. The relevance for human risk of the findings of prolactin-mediated endocrine tumors in rodents is unknown.

Mutagenesis

The mutagenic potential of aripiprazole was tested in the bacterial reverse-mutation assay, the bacterial DNA repair assay, the forward gene mutation assay in mouse lymphoma cells, the chromosomal aberration assay in Chinese hamster lung (CHL) cells, the micronucleus assay in mice, and the unscheduled DNA synthesis assay in rats. Aripiprazole and a metabolite (2,3-DCPP) were clastogenic in the chromosomal aberration assay in CHL cells with and without metabolic activation. The metabolite, 2,3-DCPP, produced increases in numerical aberrations in the assay in CHL cells in the absence of metabolic activation. A positive response was obtained in the micronucleus assay in mice; however, the response was due to a mechanism not considered relevant to humans. in vitroin vitroin vitroin vitroin vivoin vitroin vitroin vivo

Impairment of Fertility

Female rats were treated with oral doses of 2 mg/kg/day, 6 mg/kg/day, and 20 mg/kg/day (0.6 times, 2 times, and 6 times the maximum recommended human dose [MRHD] on a mg/m basis) of aripiprazole from 2 weeks prior to mating through day 7 of gestation. Estrus cycle irregularities and increased corpora lutea were seen at all doses, but no impairment of fertility was seen. Increased pre-implantation loss was seen at 6 mg/kg and 20 mg/kg and decreased fetal weight was seen at 20 mg/kg.^2

Male rats were treated with oral doses of 20 mg/kg/day, 40 mg/kg/day, and 60 mg/kg/day (6 times, 13 times, and 19 times the MRHD on a mg/m basis) of aripiprazole from 9 weeks prior to mating through mating. Disturbances in spermatogenesis were seen at 60 mg/kg and prostate atrophy was seen at 40 mg/kg and 60 mg/kg, but no impairment of fertility was seen.^2

13.2 Animal Toxicology and/or Pharmacology

Aripiprazole produced retinal degeneration in albino rats in a 26-week chronic toxicity study at a dose of 60 mg/kg and in a 2-year carcinogenicity study at doses of 40 mg/kg and 60 mg/kg. The 40 mg/kg and 60 mg/kg doses are 13 times and 19 times the maximum recommended human dose (MRHD) based on mg/m and 7 times to 14 times human exposure at MRHD based on AUC. Evaluation of the retinas of albino mice and of monkeys did not reveal evidence of retinal degeneration. Additional studies to further evaluate the mechanism have not been performed. The relevance of this finding to human risk is unknown.^2

14 CLINICAL STUDIES

14.1 Schizophrenia

Adults

The efficacy of ABILIFY in the treatment of schizophrenia was evaluated in five short-term (4-week and 6-week), placebo-controlled trials of acutely relapsed inpatients who predominantly met DSM-III/IV criteria for schizophrenia. Four of the five trials were able to distinguish aripiprazole from placebo, but one study, the smallest, did not. Three of these studies also included an active control group consisting of either risperidone (one trial) or haloperidol (two trials), but they were not designed to allow for a comparison of ABILIFY and the active comparators.

In the four positive trials for ABILIFY, four primary measures were used for assessing psychiatric signs and symptoms. The Positive and Negative Syndrome Scale (PANSS) is a multi-item inventory of general psychopathology used to evaluate the effects of drug treatment in schizophrenia. The PANSS positive subscale is a subset of items in the PANSS that rates seven positive symptoms of schizophrenia (delusions, conceptual disorganization, hallucinatory behavior, excitement, grandiosity, suspiciousness/persecution, and hostility). The PANSS negative subscale is a subset of items in the PANSS that rates seven negative symptoms of schizophrenia (blunted affect, emotional withdrawal, poor rapport, passive apathetic withdrawal, difficulty in abstract thinking, lack of spontaneity/flow of conversation, stereotyped thinking). The Clinical Global Impression (CGI) assessment reflects the impression of a skilled observer, fully familiar with the manifestations of schizophrenia, about the overall clinical state of the patient.

In a 4-week trial (n=414) comparing two fixed doses of ABILIFY (15 mg/day or 30 mg/day) to placebo, both doses of ABILIFY were superior to placebo in the PANSS total score, PANSS positive subscale, and CGI-severity score. In addition, the 15 mg dose was superior to placebo in the PANSS negative subscale. In a 4-week trial (n=404) comparing two fixed doses of ABILIFY (20 mg/day or 30 mg/day) to placebo, both doses of ABILIFY were superior to placebo in the PANSS total score, PANSS positive subscale, PANSS negative subscale, and CGI-severity score. In a 6-week trial (n=420) comparing three fixed doses of ABILIFY (10 mg/day, 15 mg/day, or 20 mg/day) to placebo, all three doses of ABILIFY were superior to placebo in the PANSS total score, PANSS positive subscale, and the PANSS negative subscale. In a 6-week trial (n=367) comparing three fixed doses of ABILIFY (2 mg/day, 5 mg/day, or 10 mg/day) to placebo, the 10 mg dose of ABILIFY was superior to placebo in the PANSS total score, the primary outcome measure of the study. The 2 mg and 5 mg doses did not demonstrate superiority to placebo on the primary outcome measure. In a fifth study, a 4-week trial (n=103) comparing ABILIFY in a range of 5 mg/day to 30 mg/day to placebo, ABILIFY was only significantly different compared to placebo in a responder analysis based on the CGI-severity score, a primary outcome for that trial.

Thus, the efficacy of 10 mg, 15 mg, 20 mg, and 30 mg daily doses was established in two studies for each dose. Among these doses, there was no evidence that the higher dose groups offered any advantage over the lowest dose group of these studies.

An examination of population subgroups did not reveal any clear evidence of differential responsiveness on the basis of age, gender, or race.

A longer-term trial enrolled 310 inpatients or outpatients meeting DSM-IV criteria for schizophrenia who were, by history, symptomatically stable on other antipsychotic medications for periods of 3 months or longer. These patients were discontinued from their antipsychotic medications and randomized to ABILIFY 15 mg/day or placebo for up to 26 weeks of observation for relapse. Relapse during the double-blind phase was defined as CGI-Improvement score of ≥5 (minimally worse), scores ≥5 (moderately severe) on the hostility or uncooperativeness items of the PANSS, or ≥20% increase in the PANSS total score. Patients receiving ABILIFY 15 mg/day experienced a significantly longer time to relapse over the subsequent 26 weeks compared to those receiving placebo.

Pediatric Patients

The efficacy of ABILIFY (aripiprazole) in the treatment of schizophrenia in pediatric patients (13 to 17 years of age) was evaluated in one 6-week, placebo-controlled trial of outpatients who met DSM-IV criteria for schizophrenia and had a PANSS score ≥70 at baseline. In this trial (n=302) comparing two fixed doses of ABILIFY (10 mg/day or 30 mg/day) to placebo, ABILIFY was titrated starting from 2 mg/day to the target dose in 5 days in the 10 mg/day treatment arm and in 11 days in the 30 mg/day treatment arm. Both doses of ABILIFY were superior to placebo in the PANSS total score, the primary outcome measure of the study. The 30 mg/day dosage was not shown to be more efficacious than the 10 mg/day dose. Although maintenance efficacy in pediatric patients has not been systematically evaluated, maintenance efficacy can be extrapolated from adult data along with comparisons of aripiprazole pharmacokinetic parameters in adult and pediatric patients.

14.2 Bipolar Disorder

Acute Treatment of Manic and Mixed Episodes

Adults

Monotherapy

The efficacy of ABILIFY as monotherapy in the acute treatment of manic episodes was established in four 3-week, placebo-controlled trials in hospitalized patients who met the DSM-IV criteria for bipolar I disorder with manic or mixed episodes. These studies included patients with or without psychotic features and two of the studies also included patients with or without a rapid-cycling course.

The primary instrument used for assessing manic symptoms was the Young Mania Rating Scale (Y-MRS), an 11-item clinician-rated scale traditionally used to assess the degree of manic symptomatology (irritability, disruptive/aggressive behavior, sleep, elevated mood, speech, increased activity, sexual interest, language/thought disorder, thought content, appearance, and insight) in a range from 0 (no manic features) to 60 (maximum score). A key secondary instrument included the Clinical Global Impression-Bipolar (CGI-BP) Scale.

In the four positive, 3-week, placebo-controlled trials (n=268; n=248; n=480; n=485) which evaluated ABILIFY in a range of 15 mg to 30 mg, once daily (with a starting dose of 15 mg/day in two studies and 30 mg/day in two studies), ABILIFY was superior to placebo in the reduction of Y-MRS total score and CGI-BP Severity of Illness score (mania). In the two studies with a starting dose of 15 mg/day, 48% and 44% of patients were on 15 mg/day at endpoint. In the two studies with a starting dose of 30 mg/day, 86% and 85% of patients were on 30 mg/day at endpoint.

Adjunctive Therapy

The efficacy of adjunctive ABILIFY with concomitant lithium or valproate in the treatment of manic or mixed episodes was established in a 6-week, placebo-controlled study (n=384) with a 2-week lead-in mood stabilizer monotherapy phase in adult patients who met DSM-IV criteria for bipolar I disorder. This study included patients with manic or mixed episodes and with or without psychotic features.

Patients were initiated on open-label lithium (0.6 mEq/L to 1.0 mEq/L) or valproate (50 μg/mL to 125 μg/mL) at therapeutic serum levels, and remained on stable doses for 2 weeks. At the end of 2 weeks, patients demonstrating inadequate response (Y-MRS total score ≥16 and ≤25% improvement on the Y-MRS total score) to lithium or valproate were randomized to receive either aripiprazole (15 mg/day or an increase to 30 mg/day as early as day 7) or placebo as adjunctive therapy with open-label lithium or valproate. In the 6-week, placebo-controlled phase, adjunctive ABILIFY starting at 15 mg/day with concomitant lithium or valproate (in a therapeutic range of 0.6 mEq/L to 1.0 mEq/L or 50 μg/mL to 125 μg/mL, respectively) was superior to lithium or valproate with adjunctive placebo in the reduction of the Y-MRS total score and CGI-BP Severity of Illness score (mania). Seventy-one percent of the patients coadministered valproate and 62% of the patients coadministered lithium were on 15 mg/day at 6-week endpoint.

Pediatric Patients

The efficacy of ABILIFY in the treatment of bipolar I disorder in pediatric patients (10 to 17 years of age) was evaluated in one 4-week, placebo-controlled trial (n=296) of outpatients who met DSM-IV criteria for bipolar I disorder manic or mixed episodes with or without psychotic features and had a Y-MRS score ≥20 at baseline. This double-blind, placebo-controlled trial compared two fixed doses of ABILIFY (10 mg/day or 30 mg/day) to placebo. The ABILIFY dose was started at 2 mg/day, which was titrated to 5 mg/day after 2 days, and to the target dose in 5 days in the 10 mg/day treatment arm, and in 13 days in the 30 mg/day treatment arm. Both doses of ABILIFY were superior to placebo in change from baseline to week 4 on the Y-MRS total score.

Maintenance Treatment of Bipolar I Disorder

Monotherapy Maintenance Therapy

A maintenance trial was conducted in adult patients meeting DSM-IV criteria for bipolar I disorder with a recent manic or mixed episode who had been stabilized on open-label ABILIFY and who had maintained a clinical response for at least 6 weeks. The first phase of this trial was an open-label stabilization period in which inpatients and outpatients were clinically stabilized and then maintained on open-label ABILIFY (15 mg/day or 30 mg/day, with a starting dose of 30 mg/day) for at least 6 consecutive weeks. One hundred sixty-one outpatients were then randomized in a double-blind fashion, to either the same dose of ABILIFY they were on at the end of the stabilization and maintenance period or placebo and were then monitored for manic or depressive relapse. During the randomization phase, ABILIFY was superior to placebo on time to the number of combined affective relapses (manic plus depressive), the primary outcome measure for this study. A total of 55 mood events were observed during the double-blind treatment phase. Nineteen were from the ABILIFY group and 36 were from the placebo group. The number of observed manic episodes in the ABILIFY group (6) were fewer than that in the placebo group (19), while the number of depressive episodes in the ABILIFY group (9) was similar to that in the placebo group (11).

An examination of population subgroups did not reveal any clear evidence of differential responsiveness on the basis of age and gender; however, there were insufficient numbers of patients in each of the ethnic groups to adequately assess inter-group differences.

Adjunctive Maintenance Therapy

An adjunctive maintenance trial was conducted in adult patients meeting DSM-IV criteria for bipolar I disorder with a recent manic or mixed episode. Patients were initiated on open-label lithium (0.6 mEq/L to 1.0 mEq/L) or valproate (50 μg/mL to 125 μg/mL) at therapeutic serum levels, and remained on stable doses for 2 weeks. At the end of 2 weeks, patients demonstrating inadequate response (Y-MRS total score ≥16 and ≤35% improvement on the Y-MRS total score) to lithium or valproate received aripiprazole with a starting dose of 15 mg/day with the option to increase to 30 mg or reduce to 10 mg as early as day 4, as adjunctive therapy with open-label lithium or valproate. Prior to randomization, patients on the combination of single-blind aripiprazole and lithium or valproate were required to maintain stability (Y-MRS and MADRS total scores ≤12) for 12 consecutive weeks. Three hundred thirty-seven patients were then randomized in a double-blind fashion, to either the same dose of ABILIFY they were on at the end of the stabilization period or placebo plus lithium or valproate and were then monitored for manic, mixed, or depressive relapse for a maximum of 52 weeks. ABILIFY was superior to placebo on the primary endpoint, time from randomization to relapse to any mood event. A mood event was defined as hospitalization for a manic, mixed, or depressive episode, study discontinuation due to lack of efficacy accompanied by Y-MRS score >16 and/or a MADRS >16, or an SAE of worsening disease accompanied by Y-MRS score >16 and/or a MADRS >16. A total of 68 mood events were observed during the double-blind treatment phase. Twenty-five were from the ABILIFY group and 43 were from the placebo group. The number of observed manic episodes in the ABILIFY group (7) were fewer than that in the placebo group (19), while the number of depressive episodes in the ABILIFY group (14) was similar to that in the placebo group (18). The Kaplan-Meier curves of the time from randomization to relapse to any mood event during the 52-week, double-blind treatment phase for ABILIFY and placebo groups are shown in Figure 1.

Figure 1: Kaplan-Meier Estimation of Proportion of Relapses to Any Mood Event for ABILIFY and Placebo Groups

An examination of population subgroups did not reveal any clear evidence of differential responsiveness on the basis of age and gender; however, there were insufficient numbers of patients in each of the ethnic groups to adequately assess inter-group differences.

14.3 Adjunctive Treatment of Major Depressive Disorder

Adults

The efficacy of ABILIFY in the adjunctive treatment of major depressive disorder (MDD) was demonstrated in two short-term (6-week), placebo-controlled trials of adult patients meeting DSM-IV criteria for MDD who had had an inadequate response to prior antidepressant therapy (1 to 3 courses) in the current episode and who had also demonstrated an inadequate response to 8 weeks of prospective antidepressant therapy (paroxetine controlled-release, venlafaxine extended-release, fluoxetine, escitalopram, or sertraline). Inadequate response for prospective treatment was defined as less than 50% improvement on the 17-item version of the Hamilton Depression Rating Scale (HAMD17), minimal HAMD17 score of 14, and a Clinical Global Impressions Improvement rating of no better than minimal improvement. Inadequate response to prior treatment was defined as less than 50% improvement as perceived by the patient after a minimum of 6 weeks of antidepressant therapy at or above the minimal effective dose.

The primary instrument used for assessing depressive symptoms was the Montgomery-Asberg Depression Rating Scale (MADRS), a 10-item clinician-rated scale used to assess the degree of depressive symptomatology (apparent sadness, reported sadness, inner tension, reduced sleep, reduced appetite, concentration difficulties, lassitude, inability to feel, pessimistic thoughts, and suicidal thoughts). The key secondary instrument was the Sheehan Disability Scale (SDS), a 3-item self-rated instrument used to assess the impact of depression on three domains of functioning (work/school, social life, and family life) with each item scored from 0 (not at all) to 10 (extreme).

In the two trials (n=381, n=362), ABILIFY was superior to placebo in reducing mean MADRS total scores. In one study, ABILIFY was also superior to placebo in reducing the mean SDS score.

In both trials, patients received ABILIFY adjunctive to antidepressants at a dose of 5 mg/day. Based on tolerability and efficacy, doses could be adjusted by 5 mg increments, one week apart. Allowable doses were: 2 mg/day, 5 mg/day, 10 mg/day, 15 mg/day, and for patients who were not on potent CYP2D6 inhibitors fluoxetine and paroxetine, 20 mg/day. The mean final dose at the end point for the two trials was 10.7 mg/day and 11.4 mg/day.

An examination of population subgroups did not reveal evidence of differential response based on age, choice of prospective antidepressant, or race. With regard to gender, a smaller mean reduction on the MADRS total score was seen in males than in females.

14.4 Irritability Associated with Autistic Disorder

Pediatric Patients

The efficacy of ABILIFY (aripiprazole) in the treatment of irritability associated with autistic disorder was established in two 8-week, placebo-controlled trials in pediatric patients (6 to 17 years of age) who met the DSM-IV criteria for autistic disorder and demonstrated behaviors such as tantrums, aggression, self-injurious behavior, or a combination of these problems. Over 75% of these subjects were under 13 years of age.

Efficacy was evaluated using two assessment scales: the Aberrant Behavior Checklist (ABC) and the Clinical Global Impression-Improvement (CGI-I) scale. The primary outcome measure in both trials was the change from baseline to endpoint in the Irritability subscale of the ABC (ABC-I). The ABC-I subscale measured the emotional and behavioral symptoms of irritability in autistic disorder, including aggression towards others, deliberate self-injuriousness, temper tantrums, and quickly changing moods.

The results of these trials are as follows:

In one of the 8-week, placebo-controlled trials, children and adolescents with autistic disorder (n=98), aged 6 to 17 years, received daily doses of placebo or ABILIFY 2 mg/day to 15 mg/day. ABILIFY, starting at 2 mg/day with increases allowed up to 15 mg/day based on clinical response, significantly improved scores on the ABC-I subscale and on the CGI-I scale compared with placebo. The mean daily dose of ABILIFY at the end of 8-week treatment was 8.6 mg/day.
In the other 8-week, placebo-controlled trial in children and adolescents with autistic disorder (n=218), aged 6 to 17 years, three fixed doses of ABILIFY (5 mg/day, 10 mg/day, or 15 mg/day) were compared to placebo. ABILIFY dosing started at 2 mg/day and was increased to 5 mg/day after one week. After a second week, it was increased to 10 mg/day for patients in the 10 mg and 15 mg dose arms, and after a third week, it was increased to 15 mg/day in the 15 mg/day treatment arm. All three doses of ABILIFY significantly improved scores on the ABC-I subscale compared with placebo.
In a clinical trial with ABILIFY conducted in children and adolescents (6 to 17 years of age), the efficacy of ABILIFY for the maintenance treatment of irritability associated with autistic disorder was not established [see Use in Specific Populations ()]. 8.4

14.5 Agitation Associated with Schizophrenia or Bipolar Mania

The efficacy of intramuscular aripiprazole for injection for the treatment of agitation was established in three short-term (24-hour), placebo-controlled trials in agitated inpatients from two diagnostic groups: schizophrenia and bipolar I disorder (manic or mixed episodes, with or without psychotic features). Each of the trials included a single active comparator treatment arm of either haloperidol injection (schizophrenia studies) or lorazepam injection (bipolar mania study). Patients could receive up to three injections during the 24-hour treatment periods; however, patients could not receive the second injection until after the initial 2-hour period when the primary efficacy measure was assessed. Patients enrolled in the trials needed to be: (1) judged by the clinical investigators as clinically agitated and clinically appropriate candidates for treatment with intramuscular medication, and (2) exhibiting a level of agitation that met or exceeded a threshold score of ≥15 on the five items comprising the Positive and Negative Syndrome Scale (PANSS) Excited Component (ie, poor impulse control, tension, hostility, uncooperativeness, and excitement items) with at least two individual item scores ≥4 using a 1-7 scoring system (1 = absent, 4 = moderate, 7 = extreme). In the studies, the mean baseline PANSS Excited Component score was 19, with scores ranging from 15 to 34 (out of a maximum score of 35), thus suggesting predominantly moderate levels of agitation with some patients experiencing mild or severe levels of agitation. The primary efficacy measure used for assessing agitation signs and symptoms in these trials was the change from baseline in the PANSS Excited Component at 2 hours post-injection. A key secondary measure was the Clinical Global Impression of Improvement (CGI-I) Scale. The results of the trials follow:

In a placebo-controlled trial in agitated inpatients predominantly meeting DSM-IV criteria for schizophrenia (n=350), four fixed aripiprazole injection doses of 1 mg, 5.25 mg, 9.75 mg, and 15 mg were evaluated. At 2 hours post-injection, the 5.25 mg, 9.75 mg, and 15 mg doses were statistically superior to placebo in the PANSS Excited Component and on the CGI-I Scale.
In a second placebo-controlled trial in agitated inpatients predominantly meeting DSM-IV criteria for schizophrenia (n=445), one fixed aripiprazole injection dose of 9.75 mg was evaluated. At 2 hours post-injection, aripiprazole for injection was statistically superior to placebo in the PANSS Excited Component and on the CGI-I Scale. In a placebo-controlled trial in agitated inpatients meeting DSM-IV criteria for bipolar I disorder (manic or mixed) (n=291), two fixed aripiprazole injection doses of 9.75 mg and 15 mg were evaluated. At 2 hours post-injection, both doses were statistically superior to placebo in the PANSS Excited Component.

Examination of population subsets (age, race, and gender) did not reveal any differential responsiveness on the basis of these subgroupings.

16 HOW SUPPLIED/STORAGE AND HANDLING

NDC:64725-0009-1 in a BOTTLE of 30 TABLETS

16.1 How Supplied

ABILIFY (aripiprazole) Tablets have markings on one side and are available in the strengths and packages listed in Table 22.®

Table 22: ABILIFY Tablet Presentations
Tablet Strength | Tablet Color/Shape | Tablet Markings | Pack Size | NDC Code
2 mg | green modified rectangle | “A-006” and “2” | Bottle of 30 | 59148-006-13
5 mg | blue modified rectangle | “A-007” and “5” | Bottle of 30 Blister of 100 | 59148-007-13 59148-007-35
10 mg | pink modified rectangle | “A-008” and “10” | Bottle of 30 Blister of 100 | 59148-008-13 59148-008-35
15 mg | yellow round | “A-009” and “15” | Bottle of 30 Blister of 100 | 59148-009-13 59148-009-35
20 mg | white round | “A-010” and “20” | Bottle of 30 Blister of 100 | 59148-010-13 59148-010-35
30 mg | pink round | “A-011” and “30” | Bottle of 30 Blister of 100 | 59148-011-13 59148-011-35

ABILIFY DISCMELT (aripiprazole) Orally Disintegrating Tablets are round tablets with markings on either side. ABILIFY DISCMELT is available in the strengths and packages listed in Table 23.®

Table 23: ABILIFY DISCMELT Orally Disintegrating Tablet Presentations
Tablet Strength | Tablet Color | Tablet Markings | Pack Size | NDC Code
10 mg | pink (with scattered specks) | “A” and “640” “10” | Blister of 30 | 59148-640-23
15 mg | yellow (with scattered specks) | “A” and “641” “15” | Blister of 30 | 59148-641-23

ABILIFY (aripiprazole) Oral Solution (1 mg/mL) is supplied in child-resistant bottles along with a calibrated oral dosing cup. ABILIFY Oral Solution is available as follows:®

150 mL bottle NDC 59148-013-15

ABILIFY (aripiprazole) Injection for intramuscular use is available as a ready-to-use, 9.75 mg/1.3 mL (7.5 mg/mL) solution in clear, Type 1 glass vials as follows:®

9.75 mg/1.3 mL single-dose vial NDC 59148-016-65

16.2 Storage

Tablets

Store at 25°C (77°F); excursions permitted between 15°C to 30°C (59°F to 86°F) [see USP Controlled Room Temperature].

Oral Solution

Store at 25°C (77°F); excursions permitted between 15°C to 30°C (59°F to 86°F) [see USP Controlled Room Temperature]. Opened bottles of ABILIFY Oral Solution can be used for up to 6 months after opening, but not beyond the expiration date on the bottle. The bottle and its contents should be discarded after the expiration date.

Injection

Store at 25°C (77°F); excursions permitted between 15°C to 30°C (59°F to 86°F) [see USP Controlled Room Temperature]. Protect from light by storing in the original container. Retain in carton until time of use.

17 PATIENT COUNSELING INFORMATION

See Medication Guide

17.1 Information for Patients

Physicians are advised to discuss the following issues with patients for whom they prescribe ABILIFY:

Increased Mortality in Elderly Patients with Dementia-Related Psychosis

Patients and caregivers should be advised that elderly patients with dementia-related psychoses treated with antipsychotic drugs are at increased risk of death. ABILIFY is not approved for elderly patients with dementia-related psychosis . [see WARNINGS AND PRECAUTIONS ] (5.1)

Suicidal Thoughts and Behaviors in Adolescents and Young Adults

Patients, their families, and their caregivers should be encouraged to be alert to the emergence of anxiety, agitation, panic attacks, insomnia, irritability, hostility, aggressiveness, impulsivity, akathisia (psychomotor restlessness), hypomania, mania, other unusual changes in behavior, worsening of depression, and suicidal ideation, especially early during antidepressant treatment and when the dose is adjusted up or down. Families and caregivers of patients should be advised to look for the emergence of such symptoms on a day-to-day basis, since changes may be abrupt. Such symptoms should be reported to the patient’s prescriber or health professional, especially if they are severe, abrupt in onset, or were not part of the patient’s presenting symptoms. Symptoms such as these may be associated with an increased risk for suicidal thinking and behavior . and indicate a need for very close monitoring and possibly changes in the medication [see WARNINGS AND PRECAUTIONS ] (5.2)

Prescribers or other health professionals should inform patients, their families, and their caregivers about the benefits and risks associated with treatment with ABILIFY and should counsel them in its appropriate use. A patient Medication Guide including information about “Antidepressant Medicines, Depression and other Serious Mental Illness, and Suicidal Thoughts or Actions” is available for ABILIFY. The prescriber or health professional should instruct patients, their families, and their caregivers to read the Medication Guide and should assist them in understanding its contents. Patients should be given the opportunity to discuss the contents of the Medication Guide and to obtain answers to any questions they may have. It should be noted that ABILIFY is not approved as a single agent for treatment of depression and has not been evaluated in pediatric major depressive disorder.

Use of Orally Disintegrating Tablet

Do not open the blister until ready to administer. For single tablet removal, open the package and peel back the foil on the blister to expose the tablet. Do not push the tablet through the foil because this could damage the tablet. Immediately upon opening the blister, using dry hands, remove the tablet and place the entire ABILIFY DISCMELT Orally Disintegrating Tablet on the tongue. Tablet disintegration occurs rapidly in saliva. It is recommended that ABILIFY DISCMELT be taken without liquid. However, if needed, it can be taken with liquid. Do not attempt to split the tablet.

Interference with Cognitive and Motor Performance

Because aripiprazole may have the potential to impair judgment, thinking, or motor skills, patients should be cautioned about operating hazardous machinery, including automobiles, until they are reasonably certain that aripiprazole therapy does not affect them adversely . [see WARNINGS AND PRECAUTIONS ] (5.9)

Pregnancy

Patients should be advised to notify their physician if they become pregnant or intend to become pregnant during therapy with ABILIFY . [see USE IN SPECIFIC POPULATIONS ] (8.1)

Nursing

Patients should be advised not to breast-feed an infant if they are taking ABILIFY . [see USE IN SPECIFIC POPULATIONS ] (8.3)

ConcomitantMedication

Patients should be advised to inform their physicians if they are taking, or plan to take, any prescription or over-the-counter drugs, since there is a potential for interactions . [see DRUG INTERACTIONS ] (7)

Alcohol

Patients should be advised to avoid alcohol while taking ABILIFY . [see DRUG INTERACTIONS ] (7.2)

Heat Exposure and Dehydration

Patients should be advised regarding appropriate care in avoiding overheating and dehydration . [see WARNINGS AND PRECAUTIONS ] (5.10)

Sugar Content

Patients should be advised that each mL of ABILIFY Oral Solution contains 400 mg of sucrose and 200 mg of fructose.

Phenylketonurics

Phenylalanine is a component of aspartame. Each ABILIFY DISCMELT Orally Disintegrating Tablet contains the following amounts: 10 mg, 1.12 mg phenylalanine and 15 mg, 1.68 mg phenylalanine.

Tablets manufactured by Otsuka Pharmaceutical Co., Ltd., Tokyo, 101-8535 Japan or Bristol-Myers Squibb Company, Princeton, NJ 08543 USA

Orally Disintegrating Tablets, Oral Solution, and Injection manufactured by Bristol-Myers Squibb Company, Princeton, NJ 08543 USA

Distributed and marketed by Otsuka America Pharmaceutical, Inc., Rockville, MD 20850 USA

ABILIFY is a trademark of Otsuka Pharmaceutical Company.

1239550B5 03US14L-1120C Rev June 2014

© 2013, Otsuka Pharmaceutical Co., Ltd., Tokyo, 101-8535 Japan

MEDICATION GUIDE

ABILIFY® (a BIL ĭ fī)

Generic name: aripiprazole

Read this Medication Guide before you start taking ABILIFY and each time you get a refill. There may be new information. This Medication Guide does not take the place of talking to your healthcare provider about your medical condition or treatment.

What is the most important information I should know about ABILIFY?

(For other side effects, also see “ ”). What are the possible side effects of ABILIFY?

Serious side effects may happen when you take ABILIFY, including:

- Medicines like ABILIFY can raise the risk of death in elderly people who have lost touch with reality (psychosis) due to confusion and memory loss (dementia). ABILIFY is not approved for the treatment of patients with dementia-related psychosis. Increased risk of death in elderly patients with dementia-related psychosis:
- Risk of suicidal thoughts or actions: Antidepressant medicines, depression and other serious mental illnesses, and suicidal thoughts or actions:
- Antidepressant medicines may increase suicidal thoughts or actions in some children, teenagers, and young adults within the first few months of treatment.
- These include people who have (or have a family history of) bipolar illness (also called manic-depressive illness) or suicidal thoughts or actions. Depression and other serious mental illnesses are the most important causes of suicidal thoughts and actions. Some people may have a particularly high risk of having suicidal thoughts or actions.
- How can I watch for and try to prevent suicidal thoughts and actions in myself or a family member?
- Pay close attention to any changes, especially sudden changes, in mood, behaviors, thoughts, or feelings. This is very important when an antidepressant medicine is started or when the dose is changed.
- Call the healthcare provider right away to report new or sudden changes in mood, behavior, thoughts, or feelings.
- Keep all follow-up visits with the healthcare provider as scheduled. Call the healthcare provider between visits as needed, especially if you have concerns about symptoms.

Call a healthcare provider right away if you or your family member has any of the following symptoms, especially if they are new, worse, or worry you:

- thoughts about suicide or dying
- attempts to commit suicide
- new or worse depression
- new or worse anxiety
- feeling very agitated or restless
- panic attacks
- trouble sleeping (insomnia)
- new or worse irritability
- acting aggressive, being angry, or violent
- acting on dangerous impulses
- an extreme increase in activity and talking (mania)
- other unusual changes in behavior or mood

What else do I need to know about antidepressant medicines?

- Stopping an antidepressant medicine suddenly can cause other symptoms. Never stop an antidepressant medicine without first talking to a healthcare provider.
- It is important to discuss all the risks of treating depression and also the risks of not treating it. Patients and their families or other caregivers should discuss all treatment choices with the healthcare provider, not just the use of antidepressants. Antidepressants are medicines used to treat depression and other illnesses.
- Talk to the healthcare provider about the side effects of the medicine prescribed for you or your family member. Antidepressant medicines have other side effects.
- Know all of the medicines that you or your family member takes. Keep a list of all medicines to show the healthcare provider. Do not start new medicines without first checking with your healthcare provider. Antidepressant medicines can interact with other medicines.
- Talk to your child's healthcare provider for more information. Not all antidepressant medicines prescribed for children are FDA approved for use in children.

What is ABILIFY?

ABILIFY is a prescription medicine used to treat:

- schizophrenia in people age 13 years and older
- bipolar I disorder in people age 10 years and older, including:
  - manic or mixed episodes that happen with bipolar I disorder
  - manic or mixed episodes that happen with bipolar I disorder, when used with the medicine lithium or valproate
  - long-term treatment of bipolar I disorder
- major depressive disorder in adults, as an add-on treatment to an antidepressant medicine when you do not get better with an antidepressant alone
- irritability associated with autistic disorder in children and adolescents ages 6 to 17 years old
- agitation associated with schizophrenia or bipolar disorder

The symptoms of schizophrenia include:

- losing touch with reality (psychosis)
- seeing things or hearing voices that are not there (hallucinations)
- believing things that are not true (delusions)
- being suspicious (paranoia)
- disorganized speech and thinking
- bizarre behavior

The symptoms of bipolar I disorder include:

- extreme mood swings that include feeling depressed and high or irritable mood
- talking too fast and too much
- impulsive behavior
- having more energy and restlessness than usual
- needing less sleep than usual

The symptoms of major depressive disorder (MDD) include:

- feeling of sadness and emptiness
- loss of interest in activities that you once enjoyed and loss of energy
- problems focusing and making decisions
- feeling of worthlessness or guilt
- changes in sleep or eating patterns
- thoughts of death or suicide

The symptoms of irritability associated with autistic disorder include:

- aggressive behavior towards others
- intentionally trying to harm oneself
- temper tantrums
- quickly changing moods

The symptoms of agitation associated with schizophrenia or bipolar disorder include:

- hostility or aggressive behavior
- agitation and inner tension
- self-exhausting behavior

What should I tell my healthcare provider before taking ABILIFY?

Before taking ABILIFY, tell your healthcare provider if you have or had:

- diabetes or high blood sugar in you or your family; your healthcare provider should check your blood sugar before you start ABILIFY and also during therapy.
- seizures (convulsions).
- low or high blood pressure.
- heart problems or stroke.
- pregnancy or plans to become pregnant. It is not known if ABILIFY will harm your unborn baby.
- breast-feeding or plans to breast-feed. ABILIFY can pass into your breast milk and may harm your baby. Talk to your healthcare provider about the best way to feed your baby if you receive ABILIFY.
- low white blood cell count.
- phenylketonuria. ABILIFY DISCMELT Orally Disintegrating Tablets contain phenylalanine.
- any other medical conditions.

, including prescription medicines, non-prescription medicines, herbal supplements, and vitamins. Tell your healthcare provider about all the medicines that you take or recently have taken

ABILIFY and other medicines may affect each other causing possible serious side effects. ABILIFY may affect the way other medicines work, and other medicines may affect how ABILIFY works.

Your healthcare provider can tell you if it is safe to take ABILIFY with your other medicines. Do not start or stop any medicines while taking ABILIFY without talking to your healthcare provider first. Know the medicines you take. Keep a list of your medicines to show your healthcare provider and pharmacist when you get a new medicine.

How should I take ABILIFY?

- Take ABILIFY exactly as your healthcare provider tells you to take it. Do not change the dose yourself. or stop taking ABILIFY
- ABILIFY can be taken with or without food.
- ABILIFY tablets should be swallowed whole.
- If you miss a dose of ABILIFY, take the missed dose as soon as you remember. If it is almost time for the next dose, just skip the missed dose and take your next dose at the regular time. Do not take two doses of ABILIFY at the same time.
- If you have been prescribed ABILIFY DISCMELT, take it as follows:
- Do not open the blister until ready to take the DISCMELT tablet.
- To remove one DISCMELT tablet, open the package and peel back the foil on the blister to expose the tablet.
- Do not push the tablet through the foil because this could damage the tablet.
- Immediately upon opening the blister, using dry hands, remove the tablet and place the entire ABILIFY DISCMELT Orally Disintegrating Tablet on the tongue.
- Tablet disintegration occurs rapidly in saliva. It is recommended that ABILIFY DISCMELT be taken without liquid. However, if needed, it can be taken with liquid.
- Do not attempt to split the DISCMELT tablet.
- If you take too much ABILIFY, call your healthcare provider or poison control center at 1-800-222-1222 right away, or go to the nearest hospital emergency room.

What should I avoid while taking ABILIFY?

- Do not drive, operate heavy machinery, or do other dangerous activities until you know how ABILIFY affects you. ABILIFY may make you drowsy.
- Do not drink alcohol while taking ABILIFY.
- Avoid getting over-heated or dehydrated.
  - Do not over-exercise.
  - In hot weather, stay inside in a cool place if possible.
  - Stay out of the sun. Do not wear too much or heavy clothing.
  - Drink plenty of water.

What are the possible side effects of ABILIFY?

Serious side effects have been reported with ABILIFY including:

Also see “What is the most important information I should know about ABILIFY?” at the beginning of this Medication Guide.

- Tell your healthcare provider right away if you have some or all of the following symptoms: high fever, stiff muscles, confusion, sweating, changes in pulse, heart rate, and blood pressure. These may be symptoms of a rare and serious condition that can lead to death. Call your healthcare provider right away if you have any of these symptoms. Neuroleptic malignant syndrome (NMS):
- Increases in blood sugar can happen in some people who take ABILIFY. Extremely high blood sugar can lead to coma or death. If you have diabetes or risk factors for diabetes (such as being overweight or a family history of diabetes), your healthcare provider should check your blood sugar before you start ABILIFY and during therapy. High blood sugar (hyperglycemia):
  Call your healthcare provider if you have any of these symptoms of high blood sugar while taking ABILIFY:
  - feel very thirsty
  - need to urinate more than usual
  - feel very hungry
  - feel weak or tired
  - feel sick to your stomach
  - feel confused, or your breath smells fruity
- Weight gain has been reported in patients taking medicines like ABILIFY, so you and your healthcare provider should check your weight regularly. For children and adolescent patients (6 to 17 years of age) weight gain should be compared against that expected with normal growth. Increase in weight:
- may lead to aspiration and choking. Difficulty swallowing:
- Call your healthcare provider about any movements you cannot control in your face, tongue, or other body parts. These may be signs of a serious condition. Tardive dyskinesia may not go away, even if you stop taking ABILIFY. Tardive dyskinesia may also start after you stop taking ABILIFY. Tardive dyskinesia:
- lightheadedness or fainting when rising too quickly from a sitting or lying position. Orthostatic hypotension (decreased blood pressure):
- Low white blood cell count
- Seizures (convulsions)

Common side effects with ABILIFY in adults include:

• nausea

• inner sense of restlessness/need to move (akathisia)

• vomiting

• anxiety

• constipation

• insomnia

• headache

• restlessness

• dizziness

Common side effects with ABILIFY in children include:

• feeling sleepy

• insomnia

• headache

• nausea

• vomiting

• stuffy nose

• fatigue

• weight gain

• increased appetite

• uncontrolled movement such as restlessness, tremor, muscle stiffness

These are not all the possible side effects of ABILIFY. For more information, ask your healthcare provider or pharmacist.

Call your doctor for medical advice about side effects. You may report side effects to FDA at 1-800-FDA-1088.

How should I store ABILIFY?

- Store ABILIFY at room temperature, between 59°F to 86°F (15°C to 30°C).
- Opened bottles of ABILIFY Oral Solution can be used for up to 6 months after opening, but not beyond the expiration date on the bottle.

Keep ABILIFY and all medicines out of the reach of children.

General information about ABILIFY

Medicines are sometimes prescribed for purposes other than those listed in a Medication Guide. Do not use ABILIFY for a condition for which it was not prescribed. Do not give ABILIFY to other people, even if they have the same condition. It may harm them.

This Medication Guide summarizes the most important information about ABILIFY. If you would like more information, talk with your healthcare provider. You can ask your healthcare provider or pharmacist for information about ABILIFY that was written for healthcare professionals. For more information about ABILIFY visit www.abilify.com.

What are the ingredients in ABILIFY?

aripiprazole Active ingredient:

Inactive ingredients:

cornstarch, hydroxypropyl cellulose, lactose monohydrate, magnesium stearate, and microcrystalline cellulose. Colorants include ferric oxide (yellow or red) and FD&C Blue No. 2 Aluminum Lake. Tablets:

acesulfame potassium, aspartame (which contains phenylalanine), calcium silicate, croscarmellose sodium, crospovidone, crème de vanilla (natural and artificial flavors), magnesium stearate, microcrystalline cellulose, silicon dioxide, tartaric acid, and xylitol. Colorants include ferric oxide (yellow or red) and FD&C Blue No. 2 Aluminum Lake. ABILIFY DISCMELT Orally Disintegrating Tablets:

disodium edetate, fructose (200 mg per mL), glycerin, dl-lactic acid, methylparaben, propylene glycol, propylparaben, sodium hydroxide, sucrose (400 mg per mL), and purified water. The oral solution is flavored with natural orange cream and other natural flavors. ABILIFY Oral Solution:

This Medication Guide has been approved by the U.S. Food and Drug Administration.

Tablets manufactured by Otsuka Pharmaceutical Co., Ltd., Tokyo, 101-8535 Japan or Bristol-Myers Squibb Company, Princeton, NJ 08543 USA

Orally Disintegrating Tablets, Oral Solution, and Injection manufactured by Bristol-Myers Squibb Company, Princeton, NJ 08543 USA

Distributed and marketed by Otsuka America Pharmaceutical, Inc., Rockville, MD 20850 USA

ABILIFY is a trademark of Otsuka Pharmaceutical Company.

1239550B5 03US14L-1120C Rev June 2014

© 2013, Otsuka Pharmaceutical Co., Ltd., Tokyo, 101-8535 Japan